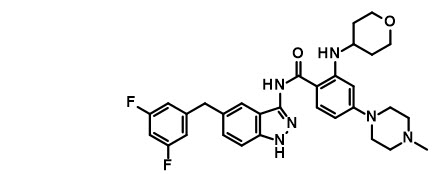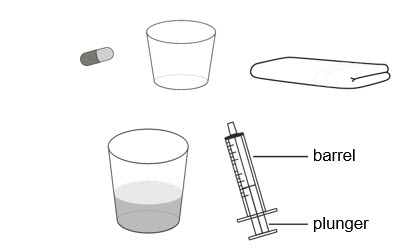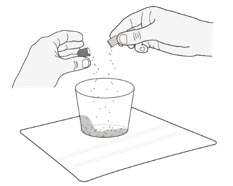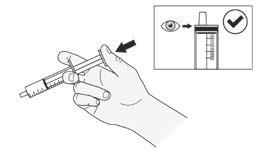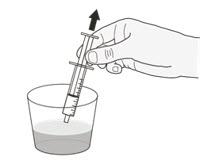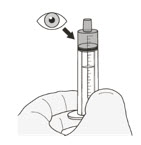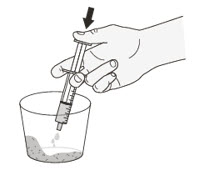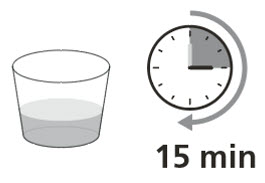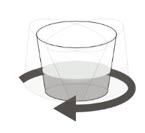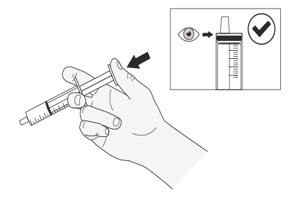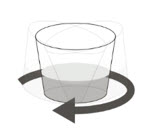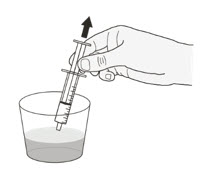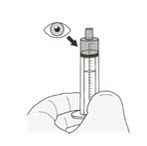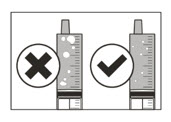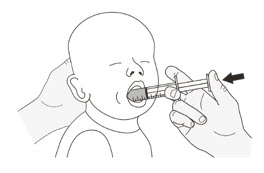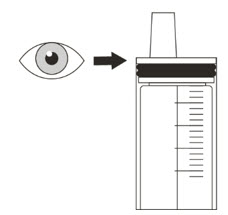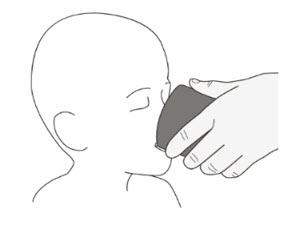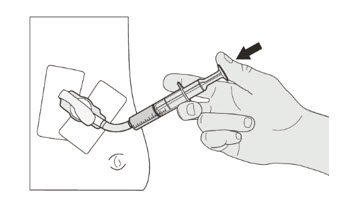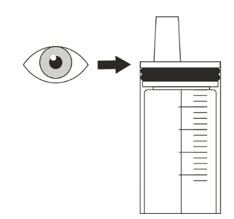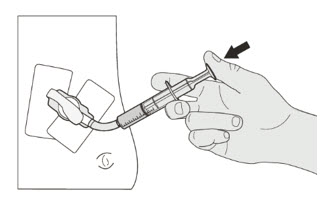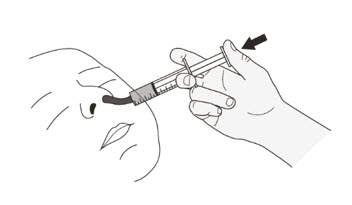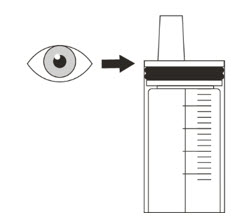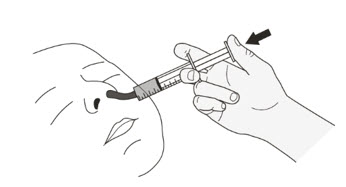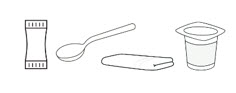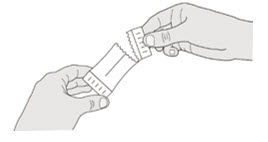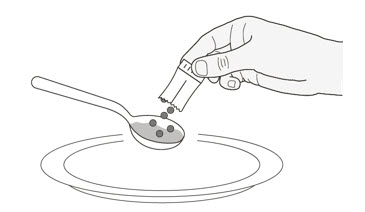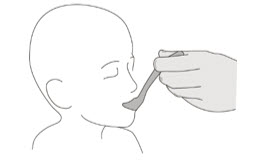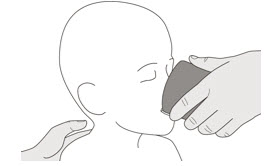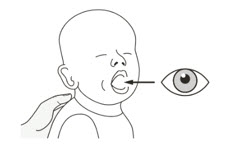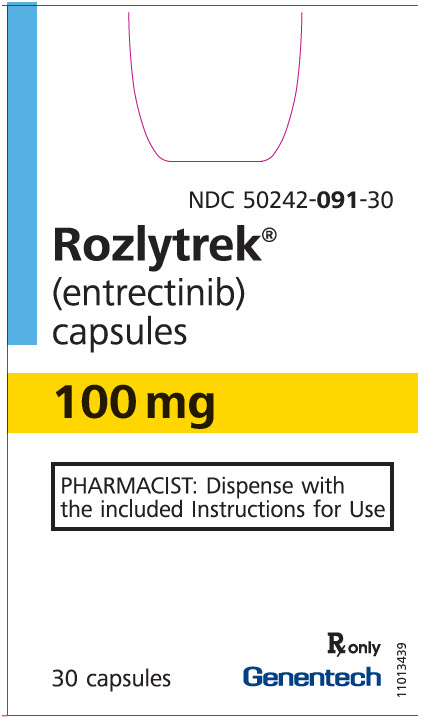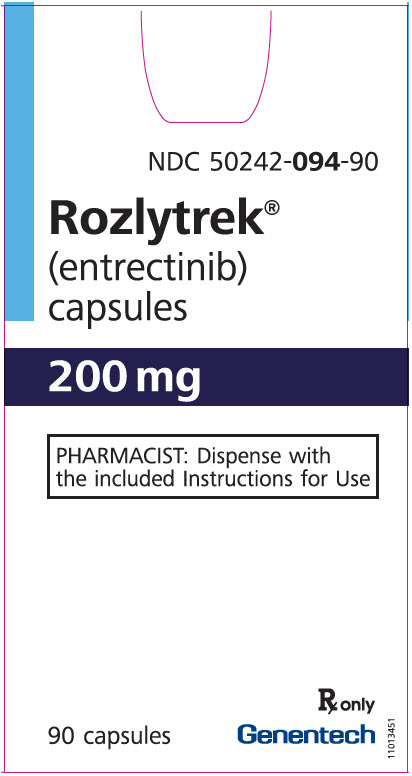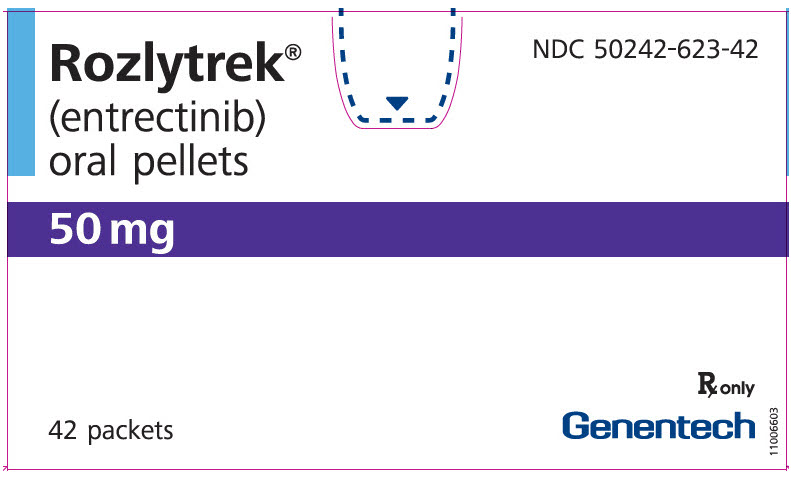 DRUG LABEL: Rozlytrek
NDC: 50242-091 | Form: CAPSULE
Manufacturer: Genentech, Inc.
Category: prescription | Type: HUMAN PRESCRIPTION DRUG LABEL
Date: 20251204

ACTIVE INGREDIENTS: ENTRECTINIB 100 mg/1 1
INACTIVE INGREDIENTS: ANHYDROUS LACTOSE; MICROCRYSTALLINE CELLULOSE; TARTARIC ACID; HYPROMELLOSE, UNSPECIFIED; CROSPOVIDONE, UNSPECIFIED; MAGNESIUM STEARATE; SILICON DIOXIDE; TITANIUM DIOXIDE; FERRIC OXIDE YELLOW; SHELLAC; PROPYLENE GLYCOL

HIGHLIGHTS OF PRESCRIBING INFORMATION

These highlights do not include all the information needed to use ROZLYTREK® safely and effectively. See full prescribing information for ROZLYTREK.
ROZLYTREK® (entrectinib) capsules, for oral use
ROZLYTREK® (entrectinib) oral pellets
Initial U.S. Approval: 2019

RECENT MAJOR CHANGES

Indications and Usage (1.2) | 10/2023
Dosage and Administration (2.1, 2.3, 2.4, 2.6, 2.7, 2.8, 2.9) | 10/2023
Dosage and Administration (2.2) | 01/2024
Warnings and Precautions (5.1) | 01/2024
Warnings and Precautions (5.3) | 10/2023

1 INDICATIONS AND USAGE

ROZLYTREK is a kinase inhibitor indicated for the treatment of:

- Adult patients with ROS1-positive metastatic non-small cell lung cancer (NSCLC) as detected by an FDA-approved test. (1.1)
- Adult and pediatric patients older than 1 month of age with solid tumors that:
  - have a neurotrophic tyrosine receptor kinase (NTRK) gene fusion, as detected by an FDA-approved test without a known acquired resistance mutation,
  - are metastatic or where surgical resection is likely to result in severe morbidity, and
  - have progressed following treatment or have no satisfactory alternative therapy.

This indication is approved under accelerated approval based on tumor response rate and durability of response. Continued approval for this indication may be contingent upon verification and description of clinical benefit in the confirmatory trials. (1.2)

2 DOSAGE AND ADMINISTRATION

- Select patients for treatment based on the presence of ROS1 rearrangement(s) or NTRK gene fusion. (2.1)
- Evaluate left ventricular ejection fraction, serum uric acid levels and QT interval and electrolytes prior to ROZLYTREK initiation. (2.2)
- Select appropriate dosage form: oral capsules, capsules prepared as an oral suspension or oral pellets. (2.3)
- Use capsules prepared as suspension for enteral tube administration. Do not use pellets for enteral tube administration. (2.3)
- Administer ROZLYTREK capsules, capsules prepared as a suspension, or pellets once daily, with or without food. (2.4)
- Adult Dosage for ROS1-Positive Non-Small Cell Lung Cancer: 600 mg orally once daily. (2.5)
- Adult and Pediatric Dosage for NTRK Gene Fusion-Positive Solid Tumors:
  - Adults: 600 mg orally once daily. (2.6)
  - Pediatric Patients: Recommended dosage is based on age and body surface area (BSA) as shown below. (2.6)
  Age | Recommended Daily Dosage
  >6 months | ≤0.50 m^2: 300 mg/m^2 0.51 to 0.80 m^2: 200 mg 0.81 to 1.10 m^2: 300 mg 1.11 to 1.50 m^2: 400 mg BSA ≥1.51 m^2: 600 mg once daily
  >1 month to ≤6 months | 250 mg/m^2 once daily
- Modify dosage of ROZLYTREK if coadministration with moderate or strong CYP3A inhibitors cannot be avoided. (2.8)
- See preparation and administration instructions. (2.9)

3 DOSAGE FORMS AND STRENGTHS

- Capsules: 100 mg and 200 mg (3)
- Pellets: 50 mg per packet (3)

4 CONTRAINDICATIONS

None. (4)

5 WARNINGS AND PRECAUTIONS

- Congestive Heart Failure (CHF): Assess left ventricular ejection fraction (LVEF) prior to initiation of ROZLYTREK. Monitor patients for clinical signs and symptoms of CHF. For patients with myocarditis, with or without a decreased ejection fraction, MRI or cardiac biopsy may be required to make the diagnosis. For new onset or worsening CHF, withhold ROZLYTREK, reassess LVEF and institute appropriate medical management. Reduce dose or permanently discontinue ROZLYTREK based on severity of CHF or worsening LVEF. (2.7, 5.1)
- Central Nervous System (CNS) Effects: CNS adverse reactions including cognitive impairment, mood disorders, dizziness, and sleep disturbances can occur with ROZLYTREK. Withhold and then resume at same or reduced dose upon improvement or permanently discontinue ROZLYTREK based on severity. (2.7, 5.2)
- Skeletal Fractures: ROZLYTREK increases the risk of fractures. Promptly evaluate patients with signs or symptoms of fractures. (5.3)
- Hepatotoxicity: Monitor liver tests, including ALT and AST, every 2 weeks during the first month of treatment, then monthly thereafter, and as clinically indicated. Withhold or permanently discontinue ROZLYTREK based on severity. If withheld, resume ROZLYTREK at same or reduced dose based on severity. (2.7, 5.4)
- Hyperuricemia: Assess serum uric acid levels prior to initiation and periodically during treatment with ROZLYTREK. Monitor patients for signs and symptoms of hyperuricemia. Initiate treatment with urate-lowering medications as clinically indicated and withhold ROZLYTREK for signs and symptoms of hyperuricemia. Resume at same or reduced dose upon improvement based on severity. (2.7, 5.5)
- QT Interval Prolongation: Monitor patients who have or who are at risk for QTc interval prolongation. Assess QT interval and electrolytes at baseline and periodically during treatment. Withhold and then resume at same or reduced dose, or permanently discontinue ROZLYTREK based on severity. (2.7, 5.6)
- Vision Disorders: Withhold for new visual changes or changes that interfere with activities of daily living until improvement or stabilization. Conduct an ophthalmological evaluation as appropriate. Resume at same or reduced dose upon improvement or stabilization. (2.7, 5.7)
- Embryo-Fetal Toxicity: Can cause fetal harm. Advise females of reproductive potential of the potential risk to a fetus and use of effective contraception. (5.8, 8.1, 8.3)

6 ADVERSE REACTIONS

The most common adverse reactions (≥ 20%) were fatigue, constipation, dysgeusia, edema, dizziness, diarrhea, nausea, dysesthesia, dyspnea, myalgia, cognitive impairment, increased weight, cough, vomiting, pyrexia, arthralgia, and vision disorders. (6.1)

To report SUSPECTED ADVERSE REACTIONS, contact Genentech at 1-888-835-2555 or FDA at 1-800-FDA-1088 or www.fda.gov/medwatch.

7 DRUG INTERACTIONS

- Moderate and Strong CYP3A Inhibitors:
  - For adult and pediatric patients 2 years and older, reduce the dose of ROZLYTREK if coadministration of moderate or strong CYP3A inhibitors cannot be avoided. (2.8, 7.1)
  - For pediatric patients less than 2 years, avoid coadministration with ROZLYTREK. (7.1)
- Moderate and Strong CYP3A Inducers: Avoid coadministration with ROZLYTREK. (7.1)
- Drugs That Prolong QTc Interval: Avoid concomitant use with ROZLYTREK. (7.2)

8 USE IN SPECIFIC POPULATIONS

- Lactation: Advise not to breastfeed. (8.2)

FULL PRESCRIBING INFORMATION

1 INDICATIONS AND USAGE

1.1 ROS1-Positive Non-Small Cell Lung Cancer

ROZLYTREK is indicated for the treatment of adult patients with ROS1-positive metastatic non-small cell lung cancer (NSCLC), as detected by an FDA-approved test.

1.2 NTRK Gene Fusion-Positive Solid Tumors

ROZLYTREK is indicated for the treatment of adult and pediatric patients older than 1 month of age with solid tumors that:

- have a neurotrophic tyrosine receptor kinase (NTRK) gene fusion, as detected by an FDA-approved test without a known acquired resistance mutation,
- are metastatic or where surgical resection is likely to result in severe morbidity, and
- have progressed following treatment or have no satisfactory alternative therapy.

This indication is approved under accelerated approval based on tumor response rate and durability of response [see Clinical Studies (14.2)]. Continued approval for this indication may be contingent upon verification and description of clinical benefit in the confirmatory trials.

2 DOSAGE AND ADMINISTRATION

2.1 Patient Selection

- Select patients for the treatment of metastatic NSCLC with ROZLYTREK based on the presence of ROS1 rearrangement(s) in tumor or plasma specimens [see Clinical Studies (14.1)]. Testing using plasma specimens is only appropriate for patients for whom tumor tissue is not available for testing.
  Information on FDA-approved tests for the detection of ROS1 rearrangement(s) in NSCLC is available at http://www.fda.gov/CompanionDiagnostics.
- Select patients for treatment of locally advanced or metastatic solid tumors with ROZLYTREK based on the presence of a NTRK gene fusion in tumor or plasma specimens [see Clinical Studies (14.2)]. Testing using plasma specimens is only appropriate for patients for whom tumor tissue is not available for testing.
  Information on FDA-approved tests for the detection of NTRK gene fusion(s) in solid tumors is available at http://www.fda.gov/CompanionDiagnostics.

2.2 Recommended Evaluation and Testing Before Initiating ROZLYTREK

Before initiating ROZLYTREK, evaluate:

- left ventricular ejection fraction (LVEF) [see Warnings and Precautions (5.1)]
- serum uric acid levels [see Warnings and Precautions (5.5)]
- QT interval and electrolytes [see Warnings and Precautions (5.6)]

2.3 ROZLYTREK Dosage Form Overview

The physician should prescribe the most appropriate dosage form of ROZLYTREK according to the dose required and patient needs.

ROZLYTREK is available in two dosage forms, and can be administered either as capsules swallowed whole, capsules made into an oral suspension (or for enteral tube administration) and as oral pellets swallowed with soft food.

ROZLYTREK Capsules 100 mg and 200 mg

- Whole capsules: For patients who can swallow whole capsules and whose doses are multiples of 100 mg.
- Capsules prepared as an oral suspension:
  - For patients who have difficulty or are unable to swallow capsules or who require enteral administration (e.g., gastric or nasogastric tube). [see Dosage and Administration (2.7)].
  - For dose increments of 10 mg, only use capsules prepared as a suspension.

ROZLYTREK Oral Pellets 50 mg per packet

- Pellets sprinkled on one or more spoonfuls of soft food:
  - For patients who have difficulty or are unable to swallow capsules but can swallow soft food and whose doses are multiples of 50 mg. [see Dosage and Administration (2.7)].
  - Do not use pellets for preparation of suspension.
  - Do not attempt to use partial quantities of pellets from 50 mg pellet packets to prepare a dose.
  - Do not use the pellet formulation for enteral tube administration as the pellets may clog the tube.

2.4 ROZLYTREK Administration Overview

- Administer ROZLYTREK capsules, capsules prepared as a suspension, or pellets once daily, with or without food.
- If a dose of ROZYTREK is missed, make up that dose unless the next dose is due within 12 hours.
- If vomiting occurs immediately after taking a dose of ROZLYTREK, repeat that dose.

2.5 ROZLYTREK Recommended Dosage for ROS1-Positive Non-Small Cell Lung Cancer

The recommended dosage of ROZLYTREK is 600 mg orally once daily with or without food until disease progression or unacceptable toxicity.

2.6 ROZLYTREK Recommended Dosage for NTRK Gene Fusion-Positive Solid Tumors

The recommended dosages of ROZLYTREK for the treatment of adult and pediatric patients with NTRK Gene Fusion-Positive Solid Tumors are provided in Table 1.

Administer the recommended dosage of ROZLYTREK capsules and oral pellets with or without food until disease progression or unacceptable toxicity.

Sprinkle ROZLYTREK oral pellets on one or more spoonfuls of soft food as a vehicle.

Table 1. Recommended dosage for Adults and Pediatric patients for the Treatment of NTRK Gene Fusion-Positive Solid Tumors
Patient Population | Recommended Dosage of ROZLYTREK | Duration of Treatment
Adults Pediatric patients with BSA ≥ 1.51 m^2: | 600 mg orally once daily | Until disease progression or unacceptable toxicity.
Pediatric patients > 6 months: | see Table 2 | Until disease progression or unacceptable toxicity.
Pediatric patients > 1 month to ≤ 6 months: | 250 mg/m^2 orally once daily [To enable dosing increments of 10 mg, capsules prepared as an oral suspension must be used [see Dosage and Administration (2.9)].] | Until disease progression or unacceptable toxicity.

The recommended dosages of ROZLYTREK for the treatment of pediatric patients older than 6 months with NTRK Gene Fusion-Positive Solid Tumors is provided in Table 2.

Table 2. Recommended dosage for Pediatric Patients Older than 6 Months for the Treatment of NTRK Gene Fusion-Positive Solid Tumors
Body Surface Area (BSA) [BSA categories and recommended dosage above are based on closely matching exposures to a target dose of 300 mg/m^2] | Recommended Dosage Orally Once Daily
≤0.50 m^2 | 300 mg/m^2 [To enable dosing increments of 10 mg, capsules prepared as an oral suspension must be used [see Dosage and Administration (2.9)].]
0.51 to 0.80 m^2 | 200 mg
0.81 to 1.10 m^2 | 300 mg
1.11 to 1.50 m^2 | 400 mg
≥ 1.51 m^2 | 600 mg

2.7 ROZLYTREK Dosage Modifications for Adverse Reactions

The recommended dosage reductions of ROZLYTREK for the management of adverse reactions for adults and pediatric patients are provided in Table 3.

Table 3. Recommended Dose Reductions for ROZLYTREK for the Management of Adverse Reactions
Starting Dose once daily | First dose reduction | Second dose reduction
250 mg/m^2 or 300 mg/m^2 | Reduce the once daily dose to two thirds of the starting dose [To enable dosing increments of 10 mg, capsules prepared as an oral suspension must be used [see Dosage and Administration (2.9)].] | Reduce the once daily dose to one third of the starting dose | Permanently discontinue ROZLYTREK in patients who are unable to tolerate ROZLYTREK after two dose reductions.
200 mg | 150 mg once daily | 100 mg once daily | Permanently discontinue ROZLYTREK in patients who are unable to tolerate ROZLYTREK after two dose reductions.
300 mg | 200 mg once daily | 100 mg once daily | Permanently discontinue ROZLYTREK in patients who are unable to tolerate ROZLYTREK after two dose reductions.
400 mg | 300 mg once daily | 200 mg once daily | Permanently discontinue ROZLYTREK in patients who are unable to tolerate ROZLYTREK after two dose reductions.
600 mg | 400 mg once daily | 200 mg once daily | Permanently discontinue ROZLYTREK in patients who are unable to tolerate ROZLYTREK after two dose reductions.

Table 4 provides the ROZLYTREK recommended dosage modifications for the management of adverse reactions.

Table 4. ROZLYTREK Dosage Modifications for the Management of Adverse Reactions
Adverse Reaction | Severity [Severity as defined by National Cancer Institute Common Terminology Criteria for Adverse Events (NCI CTCAE) version 4.0.] | Dosage Modification
Congestive Heart Failure [see Warnings and Precautions (5.1)] | Grade 2 or 3 | - Withhold ROZLYTREK until recovered to less than or equal to Grade 1. - Resume at reduced dose.
Congestive Heart Failure [see Warnings and Precautions (5.1)] | Grade 4 | - Permanently discontinue ROZLYTREK.
Central Nervous System Effects [see Warnings and Precautions (5.2)] | Intolerable Grade 2 | - Withhold ROZLYTREK until recovery to less than or equal to Grade 1 or to baseline. - Resume at same dose or reduced dose, as clinically appropriate.
Central Nervous System Effects [see Warnings and Precautions (5.2)] | Grade 3 | - Withhold ROZLYTREK until recovery to less than or equal to Grade 1 or to baseline. - Resume at reduced dose.
Central Nervous System Effects [see Warnings and Precautions (5.2)] | Grade 4 | - Permanently discontinue ROZLYTREK.
Hepatotoxicity [see Warnings and Precautions (5.4)] | Grade 3 | - Withhold ROZLYTREK until recovery to less than or equal to Grade 1 or to baseline. - Resume at same dose if resolution occurs within 4 weeks. - Permanently discontinue if adverse reaction does not resolve within 4 weeks. - Resume at a reduced dose for recurrent Grade 3 events that resolve within 4 weeks.
Hepatotoxicity [see Warnings and Precautions (5.4)] | Grade 4 | - Withhold ROZLYTREK until recovery to less than or equal to Grade 1 or to baseline. - Resume at reduced dose if resolution occurs within 4 weeks. - Permanently discontinue if adverse reaction does not resolve within 4 weeks. - Permanently discontinue for recurrent Grade 4 events.
Hepatotoxicity [see Warnings and Precautions (5.4)] | ALT or AST greater than 3 times ULN with concurrent total bilirubin greater than 1.5 times ULN (in the absence of cholestasis or hemolysis). | - Permanently discontinue ROZLYTREK.
Hyperuricemia [see Warnings and Precautions (5.5)] | Symptomatic or Grade 4 | - Initiate urate-lowering medication. - Withhold ROZLYTREK until improvement of signs or symptoms. - Resume ROZLYTREK at same or reduced dose.
QT Interval Prolongation [see Warnings and Precautions (5.6)] | QTc greater than 500 ms | - Withhold ROZLYTREK until QTc interval recovers to baseline. - Resume at same dose if factors that cause QT prolongation are identified and corrected. - Resume at reduced dose if other factors that cause QT prolongation are not identified.
QT Interval Prolongation [see Warnings and Precautions (5.6)] | Torsade de pointes; polymorphic ventricular tachycardia; signs/symptoms of serious arrhythmia | - Permanently discontinue ROZLYTREK.
Vision Disorders [see Warnings and Precautions (5.7)] | Grade 2 or above | - Withhold ROZLYTREK until improvement or stabilization. - Resume at same dose or reduced dose, as clinically appropriate.
Anemia or Neutropenia [see Adverse Reactions (6.1)] | Grade 3 or 4 | - Withhold ROZLYTREK until recovery to less than or equal to Grade 2. - Resume at the same dose or reduced dose, as clinically appropriate.
Other Adverse Reactions [see Adverse Reactions (6.1)] | Grade 3 or 4 | - Withhold ROZLYTREK until adverse reaction resolves or improves to recovery or improvement to Grade 1 or baseline. - Resume at the same or reduced dose if resolution occurs within 4 weeks. - Permanently discontinue if adverse reaction does not resolve within 4 weeks. - Permanently discontinue for recurrent Grade 4 events.

2.8 ROZLYTREK Dosage Modifications for Drug Interactions

Moderate and Strong CYP3A Inhibitors

Adults and Pediatric Patients 2 Years and Older

Avoid coadministration of ROZLYTREK with moderate or strong CYP3A inhibitors. If coadministration cannot be avoided, reduce the ROZLYTREK dose as shown in Table 5 and limit coadministration to 14 days or less.

Table 5. Recommended Dose Modifications of ROZYLTREK for Concomitant Use with Moderate or Strong CYP3A Inhibitors for Adults and Pediatric Patients 2 Years and Older
Starting dose [For pediatric patients with a starting dose less than 200 mg, avoid coadministration with moderate or strong CYP3A inhibitors] | Moderate CYP3A inhibitor | Strong CYP3A inhibitor
200 mg | 50 mg once daily | 50 mg on alternate days
300 mg | 100 mg once daily | 50 mg once daily
400 mg | 200 mg once daily | 50 mg once daily
600 mg | 200 mg once daily | 100 mg once daily

After discontinuation of a strong or moderate CYP3A inhibitor for 3 to 5 elimination half-lives, resume the ROZLYTREK dose that was taken prior to initiating the CYP3A inhibitor [see Drug Interactions (7.1), Clinical Pharmacology (12.3)].

2.9 ROZLYTREK Preparation and Administration Instructions

ROZLYTREK Capsules

Swallow capsules whole. Do not crush or chew the capsules.

ROZLYTREK Capsules Prepared as a Suspension for Oral or Enteral Tube Administration

It is recommended that a healthcare provider discuss with the patient or caregiver, the volume of water or milk to be added and oral suspension to withdraw, prior to administration of the first dose (see Table 6).

Table 6 provides the ROZLYTREK dose and volume of room temperature drinking water or milk required to prepare an oral suspension. Instruct patients or caregivers to carefully open capsule(s) and pour the contents into room temperature drinking water or milk to prepare an oral suspension. Let sit for 15 minutes.

Table 6. Preparation of ROZLYTREK Capsules as an Oral Suspension
Dose of ROZLYTREK to be administered | Dose needed for suspension (using 100 mg or 200 mg capsules, as appropriate) | Volume of water or milk to be added | Volume of oral suspension to withdraw and administer
20 mg | 100 mg | 5 mL | 1 mL
30 mg | 100 mg | 5 mL | 1.5 mL
40 mg | 100 mg | 5 mL | 2 mL
50 mg | 100 mg | 5 mL | 2.5 mL
60 mg | 100 mg | 5 mL | 3 mL
70 mg | 100 mg | 5 mL | 3.5 mL
80 mg | 100 mg | 5 mL | 4 mL
90 mg | 100 mg | 5 mL | 4.5 mL
100 mg | 100 mg | 5 mL | 5 mL
110 mg | 200 mg | 10 mL | 5.5 mL
120 mg | 200 mg | 10 mL | 6 mL
130 mg | 200 mg | 10 mL | 6.5 mL
140 mg | 200 mg | 10 mL | 7 mL
150 mg | 200 mg | 10 mL | 7.5 mL
200 mg | 200 mg | 10 mL | 10 mL
300 mg | 300 mg | 15 mL | 15 mL
400 mg | 400 mg | 20 mL | 20 mL
600 mg | 600 mg | 30 mL | 30 mL

Administer ROZLYTREK oral suspension immediately after preparation.

Discard any unused suspension if not used within 2 hours.

Instruct patients to drink water after taking the oral suspension to ensure ROZLYTREK has been completely swallowed.

Enteral Tube Administration

If enteral administration (e.g., gastric or nasogastric tube) is required, administer the oral suspension via the tube. Use an enteral tube that is 8 FR or higher to administer dosing volumes of 3 mL or higher. Instruct patients to divide dosing volumes of 3 mL or higher into at least two aliquots and flush the tube after each administration. Flush the tube with a volume of water or milk that is equal to the aliquot administered. For a dose volume of 30 mL, divide into at least three (10 mL) aliquots. The tube should be flushed with water or milk after delivering each aliquot of ROZLYTREK.

Refer to the Instructions for Use for detailed instructions on preparation and administration of ROZLYTREK capsules as an oral suspension via an enteral tube.

ROZLYTREK Oral Pellets

Sprinkle pellets on one or more spoonfuls of a soft food (e.g., applesauce, yogurt, or pudding) and take within 20 minutes of preparation. Do not crush or chew to avoid a bitter taste.

The patient should drink water after taking the pellets to ensure the drug has been completely swallowed.

Do not attempt to use partial quantities of pellets from 50 mg pellet packets to prepare a dose.

Do not use the pellet formulation for enteral tube administration as the pellets may clog the tube.

Refer to the Instructions for Use for detailed instructions on preparation and administration of ROZLYTREK oral pellets.

3 DOSAGE FORMS AND STRENGTHS

Capsules:

- 100 mg: Size 2 yellow opaque body and cap, with "ENT 100" printed in blue ink on body.
- 200 mg: Size 0 orange opaque body and cap, with "ENT 200" printed in blue ink on body.

Pellets:

- 50 mg: Supplied as brownish orange or grayish orange pellets in packets.

4 CONTRAINDICATIONS

None.

5 WARNINGS AND PRECAUTIONS

5.1 Congestive Heart Failure

Among the 355 patients who received ROZLYTREK across clinical trials, congestive heart failure (CHF) occurred in 3.4% of patients, including Grade 3 (2.3%) [see Adverse Reactions (6.1)]. In clinical trials, baseline cardiac function and routine cardiac monitoring other than electrocardiograms (ECGs) were not conducted and eligibility criteria excluded patients with symptomatic CHF, myocardial infarction, unstable angina, and coronary artery bypass graft within 3 months of study entry. Among the 12 patients with CHF, the median time to onset was 2 months (range: 11 days to 12 months). ROZLYTREK was interrupted in 6 of these patients (50%) and discontinued in 2 of these patients (17%). CHF resolved in 6 patients (50%) following interruption or discontinuation of ROZLYTREK and institution of appropriate medical management. In addition, myocarditis in the absence of CHF was documented in 0.3% of patients.

Assess left ventricular ejection fraction (LVEF) prior to initiation of ROZLYTREK. Monitor patients for clinical signs and symptoms of CHF, including shortness of breath and edema. For patients with myocarditis, with or without a decreased ejection fraction, MRI or cardiac biopsy may be required to make the diagnosis. For patients with new onset or worsening CHF, withhold ROZLYTREK, institute appropriate medical management, and reassess LVEF. Based on the severity of CHF or worsening LVEF, resume ROZLYTREK at a reduced dose upon recovery to baseline or permanently discontinue [see Dosage and Administration (2.7)].

5.2 Central Nervous System Effects

A broad spectrum of central nervous system (CNS) adverse reactions occurred in patients receiving ROZLYTREK, including cognitive impairment, mood disorders, dizziness, and sleep disturbances.

Among the 355 patients who received ROZLYTREK across clinical trials, 96 (27%) experienced cognitive impairment; symptoms occurred within 3 months of starting ROZLYTREK in 74 (77%). Cognitive impairment included cognitive disorders (8%), confusional state (7%), disturbance in attention (4.8%), memory impairment (3.7%), amnesia (2.5%), aphasia (2.3%), mental status changes (2%), hallucinations (1.1%), and delirium (0.8%). Grade 3 cognitive adverse reactions occurred in 4.5% of patients. Among the 96 patients with cognitive impairment, 13% required a dose reduction, 18% required dose interruption and 1% discontinued ROZLYTREK due to cognitive adverse reactions.

Among the 355 patients who received ROZLYTREK across clinical trials, 36 (10%) experienced mood disorders. The median time to onset of mood disorders was 1 month (range: 1 day to 9 months). Mood disorders occurring in ≥ 1% of patients included anxiety (4.8%), depression (2.8%) and agitation (2%). Grade 3 mood disorders occurred in 0.6% of patients. One completed suicide was reported 11 days after treatment had ended. Among the 36 patients who experienced mood disorders, 6% required a dose reduction, 6% required dose interruption and no patients discontinued ROZLYTREK due to mood disorders.

Dizziness occurred in 136 (38%) of the 355 patients. Among the 136 patients who experienced dizziness, Grade 3 dizziness occurred in 2.2% of patients. Ten percent of patients required a dose reduction, 7% required dose interruption and 0.7% discontinued ROZLYTREK due to dizziness.

Among the 355 patients who received ROZLYTREK across clinical trials, 51 (14%) experienced sleep disturbances. Sleep disturbances included insomnia (7%), somnolence (7%), hypersomnia (1.1%), and sleep disorder (0.3%). Grade 3 sleep disturbances occurred in 0.6% of patients. Among the 51 patients who experienced sleep disturbances, 6% required a dose reduction and no patients discontinued ROZLYTREK due to sleep disturbances.

The incidence of CNS adverse reactions was similar in patients with and without CNS metastases; however, the incidence of dizziness (38% vs 31%), headache (21% vs 13%), paresthesia (20% vs 6%), balance disorder (13% vs 4%), and confusional state (11% vs 2%) appeared to be increased in patients with CNS metastases who had received prior CNS irradiation (n = 90) compared to those who did not (n = 48).

Advise patients and caregivers of these risks with ROZLYTREK. Advise patients not to drive or operate hazardous machinery if they are experiencing CNS adverse reactions. Withhold and then resume at same or reduced dose upon improvement, or permanently discontinue ROZLYTREK based on severity [see Dosage and Administration (2.7)].

5.3 Skeletal Fractures

ROZLYTREK increases the risk of fractures. In an expanded safety population that included 338 adult patients and 76 pediatric patients who received ROZLYTREK across clinical trials, 5% of adult patients and 25% of pediatric patients experienced fractures [see Use in Specific Population (8.4)]. In adult and pediatric patients, some fractures occurred in the setting of a fall or other trauma to the affected area; in pediatric patients some fractures occurred with no trauma. In general, there was inadequate assessment for tumor involvement at the site of fracture; however, radiologic abnormalities possibly indicative of tumor involvement were reported in some adult patients. In both adult and pediatric patients, most fractures were hip or other lower extremity fractures (e.g., femoral or tibial shaft). In two pediatric patients, bilateral femoral neck fractures occurred. A total of 41 fracture events were reported in 19 pediatric patients, with 13 patients who experienced more than one occurrence of fracture. Among the 19 pediatric patients who experienced fractures, 17 patients were less than 12 years of age. Among the 41 fracture events, 27 fracture events resolved, 4 fracture events resolved with sequelae and 3 events were resolving. The median time to fracture was 3.8 months (range 0.3 to 18.5 months) in adults and 4.3 months (range: 2 months to 28.7 months) in pediatric patients. ROZLYTREK was interrupted in 41% of adults and 16% of pediatric patients who experienced fractures. Five pediatric patients discontinued treatment due to fractures.

Promptly evaluate patients with signs or symptoms (e.g., pain, changes in mobility, deformity) of fractures. There are no data on the effects of ROZLYTREK on healing of known fractures and risk of future fractures.

5.4 Hepatotoxicity

Among the 355 patients who received ROZLYTREK, increased AST of any grade occurred in 42% of patients and increased ALT of any grade occurred in 36%. Grade 3 – 4 increased AST or ALT occurred in 2.5% and 2.8% of patients, respectively; the incidence may be underestimated as 4.5% of patients had no post-treatment liver function tests [see Adverse Reactions (6.1)]. The median time to onset of increased AST was 2 weeks (range: 1 day to 29.5 months). The median time to onset of increased ALT was 2 weeks (range: 1 day to 9.2 months). Increased AST or ALT leading to dose interruptions or reductions occurred in 0.8% and 0.8% of patients, respectively. ROZLYTREK was discontinued due to increased AST or ALT in 0.8% patients.

Monitor liver tests, including ALT and AST, every 2 weeks during the first month of treatment, then monthly thereafter, and as clinically indicated. Withhold or permanently discontinue ROZLYTREK based on the severity. If withheld, resume ROZLYTREK at the same or reduced dose [see Dosage and Administration (2.7)].

5.5 Hyperuricemia

Among 355 patients who received ROZLYTREK across clinical trials, 32 patients (9%) experienced hyperuricemia reported as adverse reactions with symptoms, as well as elevated uric acid levels. Grade 4 hyperuricemia occurred in 1.7% of patients, including one patient who died due to tumor lysis syndrome. Among the 32 patients with hyperuricemic adverse reactions, 34% required urate-lowering medication to reduce uric acid levels, 6% required dose reduction and 6% required dose interruption. Hyperuricemia resolved in 73% of patients following initiation of urate-lowering medication without interruption or dose reduction of ROZLYTREK. No patients discontinued ROZLYTREK due to hyperuricemia.

Assess serum uric acid levels prior to initiation of ROZLYTREK and periodically during treatment. Monitor patients for signs and symptoms of hyperuricemia. Initiate treatment with urate-lowering medications as clinically indicated and withhold ROZLYTREK for signs and symptoms of hyperuricemia. Resume ROZLYTREK at same or reduced dose upon improvement of signs or symptoms based on severity [see Dosage and Administration (2.7)].

5.6 QT Interval Prolongation

Among the 355 patients who received ROZLYTREK across the clinical trials, 3.1% of patients with at least one post-baseline ECG assessment experienced QTcF interval prolongation of > 60 ms after starting ROZLYTREK and 0.6% had a QTcF interval > 500 ms [see Adverse Reactions (6.1), Clinical Pharmacology (12.2)].

Monitor patients who already have or who are at significant risk of developing QTc interval prolongation, including patients with known long QT syndromes, clinically significant bradyarrhythmias, severe or uncontrolled heart failure and those taking other medicinal products associated with QT prolongation. Assess QT interval and electrolytes prior to initiation of ROZLYTREK and periodically during treatment, adjusting frequency based upon risk factors such as congestive heart failure, electrolyte abnormalities, or concomitant medications known to prolong the QTc interval. Based on the severity of QTc interval prolongation, withhold ROZLYTREK and then resume at same or reduced dose, or permanently discontinue [see Dosage and Administration (2.7)].

5.7 Vision Disorders

Among the 355 patients who received ROZLYTREK across clinical trials, vision changes occurred in 21% of patients, including Grade 1 (17%), Grade 2 (2.8%) and Grade 3 (0.8%) [see Adverse Reactions (6.1)]. Vision disorders occurring in ≥ 1% included blurred vision (9%), photophobia (5%), diplopia (3.1%), visual impairment (2%), photopsia (1.1%), cataract (1.1%), and vitreous floaters (1.1%).

For patients with new visual changes or changes that interfere with activities of daily living, withhold ROZLYTREK until improvement or stabilization and conduct an ophthalmological evaluation as clinically appropriate. Upon improvement or stabilization, resume ROZLYTREK at same or reduced dose [see Dosage and Administration (2.7)].

5.8 Embryo-Fetal Toxicity

Based on literature reports in humans with congenital mutations leading to changes in TRK signaling, findings from animal studies, and its mechanism of action, ROZLYTREK can cause fetal harm when administered to a pregnant woman. Administration of entrectinib to pregnant rats resulted in malformations at exposures approximately 2.7 times the human exposure at the 600 mg dose based on area under the curve (AUC).

Advise pregnant women of the potential risk to a fetus. Advise female patients of reproductive potential to use effective contraception during treatment with ROZLYTREK and for 5 weeks following the last dose. Advise males with female partners of reproductive potential to use effective contraception during treatment with ROZLYTREK and for 3 months after the last dose [see Use in Specific Populations (8.1, 8.3)].

6 ADVERSE REACTIONS

The following clinically significant adverse reactions are described elsewhere in the labeling:

- Congestive Heart Failure [see Warnings and Precautions (5.1)]
- Central Nervous System Effects [see Warnings and Precautions (5.2)]
- Skeletal Fractures [see Warnings and Precautions (5.3)]
- Hepatotoxicity [see Warnings and Precautions (5.4)]
- Hyperuricemia [see Warnings and Precautions (5.5)]
- QT Interval Prolongation [see Warnings and Precautions (5.6)]
- Vision Disorders [see Warnings and Precautions (5.7)]

6.1 Clinical Trial Experience

Because clinical trials are conducted under widely varying conditions, adverse reaction rates observed in the clinical trials of a drug cannot be directly compared to rates in the clinical trials of another drug and may not reflect the rates observed in practice.

Data in WARNINGS AND PRECAUTIONS and below reflect exposure to ROZLYTREK in 355 patients, including 172 (48%) patients exposed for 6 months or longer and 84 (24%) patients exposed for 1 year or longer. ROZLYTREK was studied in one dose-finding trial in adults [ALKA (n = 57)], one dose-finding and activity-estimating trial in adults [STARTRK-1 (n = 76)], one dose-finding and activity-estimating trial in pediatric and adult patients [STARTRK-NG (n = 16)], and one single arm, activity-estimating trial in adults [STARTRK-2 (n = 206)].

The population characteristics were: median age 55 years (range: 4 to 86 years); 5% (n = 17) were less than 18 years of age; 55% were female; and 66% were White, 23% were Asian, and 5% were Black; 3% were Hispanic/Latino. The most common tumors (≥ 5%) were lung (56%), sarcoma (8%), and colon (5%). ROS1 gene fusions were present in 42% and NTRK gene fusions were present in 20%. Most adults (75%) received ROZLYTREK 600 mg orally once daily. The doses ranged from 100 mg/m^2 to 1600 mg/m^2 once daily in adults and 250 mg/m^2 to 750 mg/m^2 once daily in pediatric patients.

Serious adverse reactions occurred in 39% of patients. The most frequent serious adverse reactions (≥ 2%) were pneumonia (3.9%), dyspnea (3.7%), pleural effusion (3.4%), sepsis (2.5%), pulmonary embolism (2.3%), respiratory failure (2%), and pyrexia (2%). Grade 3 or 4 adverse reactions occurred in 60% of patients; the most common (≥ 2%) were lung infection (5%), increased weight (7%), dyspnea (6%), fatigue/asthenia (5%), cognitive disorders (4.5%), syncope (2.5%), pulmonary embolism (3.4%), hypoxia (3.4%), pleural effusion (3.1%), hypotension (2.8%), diarrhea (2%), and urinary tract infection (2.5%). Fatal events included dyspnea (0.6%), pneumonia (0.6%), sepsis (0.6%), completed suicide (0.3%), large intestine perforation (0.3%) and tumor lysis syndrome (0.3%). One patient developed Grade 4 myocarditis after one dose of ROZLYTREK which resolved after discontinuation of ROZLYTREK and administration of high-dose corticosteroids.

Permanent discontinuation due to an adverse reaction occurred in 9% of patients who received ROZLYTREK. The most frequent adverse reactions (< 1% each) that resulted in permanent discontinuation were pneumonia, cardio-respiratory arrest, dyspnea, and fatigue.

Dose interruptions due to adverse reactions occurred in 46% of patients. The most frequent adverse reactions (≥ 2%) that resulted in interruption were increased blood creatinine (4%), fatigue (3.7%), anemia (3.1%), diarrhea (2.8%), pyrexia (2.8%), dizziness (2.5%), dyspnea (2.3%), nausea (2.3%), pneumonia (2.3%), cognitive disorder (2%) and neutropenia (2%).

Dose reductions due to adverse reactions occurred in 29% of patients who received ROZLYTREK. The most frequent adverse reactions resulting in dose reductions (≥ 1%) were dizziness (3.9%), increased blood creatinine (3.1%), fatigue (2.3%), anemia (1.7%), and increased weight (1.4%).

The most common adverse reactions (≥ 20%) were fatigue, constipation, dysgeusia, edema, dizziness, diarrhea, nausea, dysesthesia, dyspnea, myalgia, cognitive impairment, increased weight, cough, vomiting, pyrexia, arthralgia and vision disorders.

Table 7 summarizes the adverse reactions observed in these 355 patients.

Table 7. Adverse Reactions (≥ 10%) in Patients Receiving ROZLYTREK in ALKA, STARTRK-1, STARTRK-2, and STARTRK-NG
Adverse Reactions | ROZLYTREK n = 355
Adverse Reactions | All Grades (%) | Grade ≥ 3 [Grades 3 – 5, inclusive of fatal adverse reactions, including 2 events of pneumonia and 2 events of dyspnea.] (%)
General
Fatigue [Includes fatigue, asthenia] | 48 | 5
Edema [Includes face edema, fluid retention, generalized edema, localized edema, edema, edema peripheral, peripheral swelling] | 40 | 1.1
Pyrexia | 21 | 0.8
Gastrointestinal
Constipation | 46 | 0.6
Diarrhea | 35 | 2.0
Nausea | 34 | 0.3
Vomiting | 24 | 0.8
Abdominal pain [Includes abdominal pain upper, abdominal pain, lower abdominal discomfort, abdominal tenderness] | 16 | 0.6
Nervous System
Dysgeusia | 44 | 0.3
Dizziness [Includes dizziness, vertigo, dizziness postural] | 38 | 0.8
Dysesthesia [Includes paresthesia, hyperesthesia, hypoesthesia, dysesthesia, oral hypoesthesia, palmar-plantar erythrodysesthesia, oral paresthesia, genital hypoesthesia] | 34 | 0.3
Cognitive impairment [Includes amnesia, aphasia, cognitive disorder, confusional state, delirium, disturbance in attention, hallucinations, visual hallucination, memory impairment, mental disorder, mental status changes] | 27 | 4.5
Peripheral sensory neuropathy [Includes neuralgia, neuropathy peripheral, peripheral motor neuropathy, peripheral sensory neuropathy] | 18 | 1.1
Headache | 18 | 0.3
Ataxia [Includes ataxia, balance disorder, gait disturbances] | 17 | 0.8
Sleep [Includes hypersomnia, insomnia, sleep disorder, somnolence] | 14 | 0.6
Mood disorders [Includes anxiety, affect lability, affective disorder, agitation, depressed mood, euphoric mood, mood altered, mood swings, irritability, depression, persistent depressive disorder, psychomotor retardation] | 10 | 0.6
Respiratory, Thoracic and Mediastinal
Dyspnea | 30 | 6
Cough | 24 | 0.3
Musculoskeletal and Connective Tissue
Myalgia [Includes musculoskeletal pain, musculoskeletal chest pain, myalgia, neck pain] | 28 | 1.1
Arthralgia | 21 | 0.6
Muscular weakness | 12 | 0.8
Back pain | 12 | 1
Pain in extremity | 11 | 0.3
Metabolism and Nutritional
Increased weight | 25 | 7
Decreased appetite | 13 | 0.3
Dehydration | 10 | 1.1
Eye
Vision disorders [Includes blindness, cataract, cortical cataract, corneal erosion, diplopia, eye disorder, photophobia, photopsia, retinal hemorrhage, vision blurred, visual impairment, vitreous adhesions, vitreous detachment, vitreous floaters] | 21 | 0.8
Infections
Urinary tract infection | 13 | 2.3
Lung infection [Includes lower respiratory tract infection, lung infection, pneumonia, respiratory tract infection] | 10 | 6
Vascular
Hypotension [Includes hypotension, orthostatic hypotension] | 18 | 2.8
Skin and Subcutaneous Tissue
Rash [Includes rash, rash maculopapular, rash pruritic, rash erythematous, rash papular] | 11 | 0.8

Clinically relevant adverse reactions occurring in ≤ 10% of patients include dysphagia (10%), fall (8%), pleural effusion (8%), fractures (6%), hypoxia (4.2%), pulmonary embolism (3.9%), syncope (3.9%), congestive heart failure (3.4%), and QT prolongation (3.1%).

Table 8 summarizes the laboratory abnormalities.

Table 8. Laboratory Abnormalities (≥ 20%) Worsening from Baseline in Patients Receiving ROZLYTREK in ALKA, STARTRK-1, STARTRK-2, and STARTRK-NG
Laboratory Abnormality | ROZLYTREK NCI CTCAE Grade
Laboratory Abnormality | All Grades (%) [Denominator for each laboratory parameter is based on the number of patients with a baseline and post-treatment laboratory value available which ranged from 111 to 346 patients.] | Grade 3 or 4 (%)
Chemistry
Increased creatinine [Based on NCI CTCAE v5.0] | 73 | 2.1
Hyperuricemia | 52 | 10
Increased AST | 44 | 2.7
Increased ALT | 38 | 2.9
Hypernatremia | 35 | 0.9
Hypocalcemia | 34 | 1.8
Hypophosphatemia | 30 | 7
Increased lipase | 28 | 10
Hypoalbuminemia | 28 | 2.9
Increased amylase | 26 | 5.4
Hyperkalemia | 25 | 1.5
Increased alkaline phosphatase | 25 | 0.9
Hyperglycemia [NE = Not evaluable. Grade 1 and 2 could not be determined per NCI CTCAE v5.0, as fasting glucose values were not collected] | NE | 3.8
Hematology
Anemia | 67 | 9
Lymphopenia | 40 | 12
Neutropenia | 28 | 7
AST: Aspartate Aminotransferase; ALT: Alanine Aminotransferase

Safety in Pediatric Patients

The safety of ROZLYTREK was evaluated was evaluated in pediatric patients with unresectable or metastatic solid tumors with a NTRK gene fusion enrolled in one of three multicenter, open-label clinical trials: STARTRK-NG (n=68), TAPISTRY (n=6) and STARTRK-2 (n=2). Patients received ROZLYTREK 20 mg to 600 mg based on body surface area (BSA) orally or via enteral feeding tube once daily in 4-week cycles until unacceptable toxicity or disease progression. Among patients who received ROZLYTREK, 58% were exposed for 6 months or longer and 38% were exposed for greater than one year.

The median age of patients who received ROZLYTREK was 6 years (range: 0 to 17); 51% were females; 68% were White, 18% Asian, 7% Black or African American, and 7% were other races.

Serious adverse reactions occurred in 45% of patients who received ROZLYTREK. Serious adverse reactions in > 2% of patients included skeletal fractures (12%), pneumonia (5%), pyrexia (5%), hydrocephalus (5%), device related infection (4%), hypoxia (4%), dyspnea (3%), headache (3%), gait disturbance (3%), pain (3%), upper respiratory infection (3%), and sepsis (3%).

Permanent discontinuation of ROZLYTREK due to an adverse reaction occurred in 13% of patients. Adverse reactions which resulted in permanent discontinuation of ROZLYTREK in > 2% of patients included skeletal fracture.

Dosage interruptions of ROZLYTREK due to an adverse reaction occurred in 39% of patients. Adverse reactions which required dosage interruption in > 5% of patients included decreased neutrophil count, pyrexia, vomiting, and diarrhea.

Dose reductions of ROZLYTREK due to an adverse reaction occurred in 21% of patients. Adverse reactions which required dose reductions in > 2% of patients included increased blood creatinine and increased weight.

Table 9 summarizes the adverse reactions in STARTRK-NG (n=68), TAPISTRY (n=6) and STARTRK-2 (n=2).

Table 9. Adverse Reactions (≥20%) in Pediatric Patients Who Received ROZLYTREK in STARTRK-NG, TAPISTRY and STARTRK-2
Adverse Reaction | ROZLYTREK (n=76)
Adverse Reaction | All Grades (%) | Grade 3 or 4 (%)
General Disorders
Pyrexia | 43 | 1.3
Fatigue [Includes fatigue, asthenia] | 30 | 2.6
Gastrointestinal Disorders
Constipation | 41 | 1.3
Vomiting | 38 | 0
Diarrhea | 37 | 0
Nausea | 34 | 0
Abdominal Pain | 20 | 2.6
Investigations
Increased Weight | 39 | 18
Respiratory, Thoracic And Mediastinal Disorders
Cough | 33 | 1.3
Nasal Congestion | 20 | 0
Musculoskeletal And Connective Tissue Disorders
Pain in Extremity | 26 | 2.6
Skeletal Fracture [Includes clavicle fracture, tibia fracture, femur fracture, fibula fracture, foot fracture, fracture, pathological fracture, limb fracture, lower limb fracture, pelvic fracture, spinal compression fracture, stress fracture, ulna fracture] | 25 | 11
Metabolism And Nutrition Disorders
Decreased Appetite | 24 | 1.3
Nervous System Disorders
Headache | 22 | 2.6
Infections
Upper Respiratory Tract Infection | 20 | 1.3
Urinary Tract Infection | 20 | 2.6

Clinically relevant adverse reactions in <20% of patients who received ROZLYTREK included pruritus, rash, urinary incontinence, eye pain and photophobia.

Tables 10 summarizes the laboratory abnormalities in STARTRK-NG (n=68), TAPISTRY (n=6) and STARTRK-2 (n=2).

Table 10. Select Laboratory Abnormalities (≥20%) That Worsened from Baseline in Pediatric Patients Who Received ROZLYTREK in STARTRK-NG, TAPISTRY and STARTRK-2
Laboratory Abnormality | ROZLYTREK [The denominator used to calculate the rate varied from 67 to 76 based on the number of patients with a baseline value and at least one post-treatment value. All values based on NCI CTCAE v5.0]
Laboratory Abnormality | All Grades (%) | Grade 3 or 4 (%)
Hematology
Decreased Hemoglobin | 53 | 7
Decreased Neutrophils | 53 | 22
Decreased Leukocytes | 46 | 1.3
Increased Lymphocytes | 33 | 3
Chemistry
Increased Creatinine | 84 | 5
Increased AST | 61 | 2.7
Increased ALT | 53 | 2.6
Increased Sodium | 38 | 1.4
Increased Magnesium | 32 | 5
Increased Alkaline Phosphatase | 25 | 0
Decreased Glucose | 26 | 0
Increased Potassium | 25 | 2.7
Decreased Albumin | 24 | 9
Increased Calcium | 21 | 8
Increased Bilirubin | 20 | 8
AST: Aspartate Aminotransferase; ALT: Alanine Aminotransferase

Other clinically relevant laboratory abnormalities in patients who received ROZLYTREK included decreased phosphorous.

7 DRUG INTERACTIONS

7.1 Effect of Other Drugs on ROZLYTREK

Moderate and Strong CYP3A Inhibitors

Adults and Pediatric Patients 2 Years and Older

Coadministration of ROZLYTREK with a strong or moderate CYP3A inhibitor increases entrectinib plasma concentrations [see Clinical Pharmacology (12.3)], which could increase the frequency or severity of adverse reactions. Avoid coadministration of strong or moderate CYP3A inhibitors with ROZLYTREK. If coadministration is unavoidable, reduce the ROZLYTREK dose [see Dosage and Administration (2.8), Clinical Pharmacology (12.3)].

Pediatric Patients less than 2 Years

Avoid coadministration of ROZLYTREK with moderate or strong CYP3A inhibitors [see Clinical Pharmacology (12.3)].

Avoid grapefruit products during treatment with ROZLYTREK, as they contain inhibitors of CYP3A.

Moderate and Strong CYP3A Inducers

Coadministration of ROZLYTREK with a strong or moderate CYP3A inducer decreases entrectinib plasma concentrations [see Clinical Pharmacology (12.3)], which may reduce ROZLYTREK efficacy. Avoid coadministration of strong and moderate CYP3A inducers with ROZLYTREK.

7.2 Drugs That Prolong QTc Interval

QTc interval prolongation can occur with ROZLYTREK. Avoid coadministration of ROZLYTREK with other products with a known potential to prolong QT/QTc interval [see Warnings and Precautions (5.6), Clinical Pharmacology (12.2)].

8 USE IN SPECIFIC POPULATIONS

8.1 Pregnancy

Risk Summary

Based on literature reports in humans with congenital mutations leading to changes in TRK signaling, findings from animal studies, and its mechanism of action [see Clinical Pharmacology (12.1)], ROZLYTREK can cause fetal harm when administered to a pregnant woman. There are no available data on ROZLYTREK use in pregnant women. Administration of entrectinib to pregnant rats during the period of organogenesis resulted in malformations at maternal exposures approximately 2.7 times the human exposure at the 600 mg dose (see Data). Advise pregnant women of the potential risk to a fetus.

In the U.S. general population, the estimated background risk of major birth defects and miscarriage in clinically recognized pregnancies is 2% to 4% and 15% to 20%, respectively.

Data

Human Data

Published reports of individuals with congenital mutations in TRK pathway proteins suggest that decreases in TRK-mediated signaling are correlated with obesity, developmental delays, cognitive impairment, insensitivity to pain, and anhidrosis.

Animal Data

Entrectinib administration to pregnant rats during the period of organogenesis at a dose of 200 mg/kg [resulting in exposures up to 2.7 times the human exposure (AUC) at the 600 mg dose] resulted in maternal toxicity and fetal malformations including body closure defects (omphalocele and gastroschisis) and malformations of the vertebrae, ribs, and limbs (micromelia and adactyly), but not embryolethality. Lower fetal weights and reduced skeletal ossification occurred at doses ≥ 12.5 and 50 mg/kg [approximately 0.2 and 0.9 times the human exposure (AUC) at the 600 mg dose], respectively.

8.2 Lactation

Risk Summary

There are no data on the presence of entrectinib or its metabolites in human milk or their effects on either the breastfed child or on milk production. Because of the potential serious adverse reactions in breastfed children from ROZLYTREK, advise a lactating woman to discontinue breastfeeding during treatment with ROZLYTREK and for 7 days after the last dose.

8.3 Females and Males of Reproductive Potential

Pregnancy Testing

Verify the pregnancy status of females of reproductive potential prior to initiating ROZLYTREK [see Use in Specific Populations (8.1)].

Contraception

ROZLYTREK can cause embryo-fetal harm when administered to a pregnant woman [see Use in Specific Populations (8.1)].

Females

Advise female patients of reproductive potential to use effective contraception during treatment with ROZLYTREK and for at least 5 weeks following the last dose [see Use in Specific Populations (8.1)].

Males

Advise male patients with female partners of reproductive potential to use effective contraception during treatment with ROZLYTREK and for 3 months following the last dose [see Nonclinical Toxicology (13.1)].

8.4 Pediatric Use

The safety and effectiveness of ROZLYTREK have been established in pediatric patients older than 1 month of age [Clinical Studies (14.2)]. Use of ROZLYTREK in these age groups is supported by evidence from adequate and well-controlled studies of ROZLYTREK in adults and pediatric patients with additional population pharmacokinetic data demonstrating that the exposure of drug substance in pediatric patients greater than 1 month of age is expected to be in the adult range, and that the course of disease is sufficiently similar in adult and pediatric patients to allow extrapolation of data in adults to pediatric patients.

The safety and effectiveness of ROZLYTREK have not been established in pediatric patients with ROS1-positive NSCLC.

Juvenile Animal Toxicity Data

In a 13-week juvenile rat toxicology study, animals were dosed daily from post-natal day 7 to day 97 (approximately equivalent to neonate to adulthood). Entrectinib resulted in:

- decreased body weight gain and delayed sexual maturation at doses ≥ 4 mg/kg/day (approximately 0.06 times the human exposure (AUC) at the 600 mg dose),
- deficits in neurobehavioral assessments including functional observational battery and learning and memory (at doses ≥ 8 mg/kg/day, approximately 0.14 times the human exposure at the 600 mg dose), and
- decreased femur length at doses ≥ 16 mg/kg/day (approximately 0.18 times the human exposure at the 600 mg dose).

8.5 Geriatric Use

Of the 355 patients who received ROZLYTREK across clinical trials, 25% were 65 years or older, and 5% were 75 years of age or older. Clinical studies of ROZLYTREK did not include sufficient numbers of geriatric patients to determine whether they respond differently from younger patients.

8.6 Renal Impairment

No dose adjustment is recommended for patients with mild or moderate renal impairment (CLcr 30 to < 90 mL/min calculated by Cockcroft-Gault equation). ROZLYTREK has not been studied in patients with severe renal impairment (CLcr < 30 mL/min) [see Clinical Pharmacology (12.3)].

8.7 Hepatic Impairment

The effect of moderate hepatic impairment (total bilirubin > 1.5 – 3.0 times ULN with any aspartate aminotransferase) or severe hepatic impairment (total bilirubin >3.0 times ULN with any aspartate aminotransferase) on the safety of ROZLYTREK at the recommended dosage is unknown. Consider the risk-benefit profile of ROZLYTREK prior to determining whether to administer ROZLYTREK to patients with moderate to severe hepatic impairment. Monitor for ROZLYTREK adverse reactions in patients with hepatic impairment more frequently since these patients may be at increased risk for adverse reactions [see Clinical Pharmacology (12.3)].

11 DESCRIPTION

Entrectinib is a kinase inhibitor. The molecular formula for entrectinib is C31H34F2N6O2 and the molecular weight is 560.64 Daltons. The chemical name is N-[5-(3,5-difluorobenzyl)-1H-indazol-3-yl]-4-(4-methylpiperazin-1-yl)-2-(tetrahydro-2H-pyran-4-ylamino) benzamide. The chemical structure of entrectinib is as follows:

Entrectinib is white to pale pink powder.

Capsules:

ROZLYTREK (entrectinib) capsules for oral use are supplied as printed hard-shell capsules containing 100 mg (yellow opaque HPMC capsule) or 200 mg of entrectinib (orange opaque HPMC capsule). Inactive ingredients are tartaric acid, lactose anhydrous, hypromellose, crospovidone, microcrystalline cellulose, colloidal silicon dioxide, and magnesium stearate.

The yellow opaque capsule shell contains hypromellose, titanium dioxide, and yellow iron oxide. The orange opaque capsule shell contains hypromellose, titanium dioxide, and FD&C yellow #6. The printing ink contains shellac, propylene glycol, strong ammonia solution, and FD&C blue #2 aluminum lake.

Pellets:

ROZLYTREK (entrectinib) oral pellets are supplied as brownish orange or grayish orange, round film-coated pellets in packets. Each packet contains 50 mg of entrectinib and the following inactive ingredients: tartaric acid, microcrystalline cellulose, colloidal silicon dioxide, croscarmellose sodium, sodium stearyl fumarate, mannitol, and magnesium stearate.

The film-coating contains polyvinyl alcohol (partially hydrolyzed), titanium dioxide, polyethylene glycol 3350, talc, yellow iron oxide, red iron oxide, and ferrosoferric oxide.

12 CLINICAL PHARMACOLOGY

12.1 Mechanism of Action

Entrectinib is an inhibitor of the tropomyosin receptor tyrosine kinases (TRK) TRKA, TRKB, and TRKC (encoded by the neurotrophic tyrosine receptor kinase [NTRK] genes NTRK1, NTRK2, and NTRK3, respectively), proto-oncogene tyrosine-protein kinase ROS1 (ROS1), and anaplastic lymphoma kinase (ALK) with IC50 values of 0.1 to 2 nM. Entrectinib also inhibits JAK2 and TNK2 with IC50 values > 5 nM. The major active metabolite of entrectinib, M5, showed similar in vitro activity against TRK, ROS1, and ALK.

Fusion proteins that include TRK, ROS1, or ALK kinase domains can drive tumorigenic potential through hyperactivation of downstream signaling pathways leading to unconstrained cell proliferation. Entrectinib demonstrated in vitro and in vivo inhibition of cancer cell lines derived from multiple tumor types harboring NTRK, ROS1, and ALK fusion genes.

Entrectinib demonstrated steady-state brain-to-plasma concentration ratios of 0.4 – 2.2 in multiple animal species (mice, rats, and dogs) and demonstrated in vivo anti-tumor activity in mice with intracranial implantation of TRKA- and ALK-driven tumor cell lines.

12.2 Pharmacodynamics

Entrectinib exposure-response relationships and the time course of pharmacodynamic responses are unknown.

Cardiac Electrophysiology

Across clinical trials, 3.1% of 355 patients, who received ROZLYTREK at doses ranging from 100 mg to 2600 mg daily under fasting or fed conditions (75% received 600 mg orally once daily) and had at least one post-baseline ECG assessment, experienced QTcF interval prolongation of > 60 ms after starting ROZLYTREK and 0.6% had a QTc interval > 500 ms [see Warnings and Precautions (5.6)].

12.3 Pharmacokinetics

The pharmacokinetics for entrectinib and its pharmacologically active major circulating metabolite M5 were characterized in adult patients with ROS1-positive NSCLC, NTRK gene fusion-positive solid tumors, and healthy subjects. The pharmacokinetics of entrectinib and M5 are linear and are not dose-dependent or time-dependent. Steady state is achieved within one week for entrectinib and two weeks for M5 following daily administration of ROZLYTREK. The pharmacokinetic parameters for entrectinib and M5 are described in Table 11.

Table 11. Pharmacokinetic Parameters for Entrectinib and Metabolite M5
Parameter | Entrectinib Mean [Geometric mean] (% CV) | M5 Mean (% CV)
AUCD1 (nM*h) | 31800 (48%) | 10200 (82%)
AUCss (nM*h) | 48000 (77%) | 24000 (97%)
CmaxD1 (nM) | 2250 (58%) | 622 (79%)
Cmaxss (nM) | 3130 (80%) | 1250 (90%)
Racc(AUC) | 1.55 (49%) | 2.84 (93%)

Absorption

The maximum entrectinib plasma concentration was reached 4 – 6 hours after oral administration of a 600 mg dose.

Entrectinib exposure following a single oral dose (600 mg) of ROZLYTREK oral pellets was not clinically significant compared to ROZLYTREK capsule administered with a light meal (250 calories: 25% fat) in healthy subjects. In STARTRK-2, STARTRK-NG and TAPISTRY studies, ROZLYTREK was administered without regard to food in patients.

Entrectinib exposure of a single dose (600 mg) of ROZLYTREK capsules as a suspension with water or milk, administered orally or through a nasogastric or gastric tube, was not clinically significant compared to administration of intact ROZLYTREK capsules in healthy subjects under fasted conditions.

Effect of Food

A high-fat (approximately 50% of total caloric content), high-calorie (approximately 800 to 1000 calories) meal did not have a significant effect on entrectinib exposure of ROZLYTREK capsules.

Distribution

Entrectinib and its active major metabolite M5 are both > 99% bound to human plasma proteins in vitro.

The estimated apparent volume of distribution (V/F) was 551 L and 81.1 L for entrectinib and M5, respectively.

Elimination

The estimated apparent clearance (CL/F) was 19.6 L/h and 52.4 L/h for entrectinib and M5, respectively. The elimination half-lives of entrectinib and M5 were estimated to be 20 and 40 hours, respectively.

Metabolism

Entrectinib is metabolized primarily by CYP3A4 (~76%). The active metabolite M5 (formed by CYP3A4) is the only major active circulating metabolite identified. M5 has similar pharmacological potency to entrectinib in vitro and circulating M5 exposures at steady-state in patients were 40% of the corresponding entrectinib exposure.

Excretion

Following oral administration of a single oral dose of [^14C]-labeled entrectinib, 83% of radioactivity was excreted in feces (36% of the dose as unchanged entrectinib and 22% as M5) with minimal excretion in urine (3%).

Specific Populations

No clinically significant differences in the pharmacokinetics of entrectinib were observed based on sex, race (White, Asian and Black), mild to moderate renal impairment (CLcr 30 to < 90 mL/min) and mild hepatic impairment (total bilirubin ≤ ULN with aspartate aminotransferase > ULN or total bilirubin > 1.0 – 1.5 times ULN with any aspartate aminotransferase). The impact of severe renal impairment on the pharmacokinetics of entrectinib is unknown.

Hepatic Impairment

Following administration of a single oral dose of ROZLYTREK 100 mg (1/6 of the recommended dose), the entrectinib AUCINF was increased by 39% for the mild, 39% for the moderate, and 23% for the severe hepatic impairment groups compared to the normal hepatic function group. The combined AUClast of entrectinib and M5 was increased by 16% for the mild, 16% for the moderate, and 4% for the severe hepatic impairment groups compared to the normal hepatic function group. Large variability in systemic exposure of entrectinib was observed in the hepatic impairment groups.

Pediatric Patients > 6 months

In pediatric patients older than 6 months administered 300 mg/m^2 (based on BSA) of ROZLYTREK once daily, systemic exposure of the sum of entrectinib and M5 in pediatric patients receiving 300 mg/m^2 of ROZLYTREK once daily is within the range of the adults treated with 600 mg of ROZLYTREK once daily.

The available efficacy and safety data also confirm the adequacy of the recommended doses [see Use in Specific Populations (8.4)].

Pediatric Patients > 1 to ≤ 6 months

In pediatric patients > 1 to ≤ 6 months administered 250 mg/m^2 (based on BSA) of ROZLYTREK once daily, systemic exposure of the sum of entrectinib and M5 in pediatric patients was at the lower range of the adults administered 600 mg of ROZLYTREK once daily.

The available efficacy and safety data also confirm the adequacy of the recommended doses [see Use in Specific Populations (8.4)].

Drug Interaction Studies

Clinical Studies

Effect of CYP3A Inhibitors on Entrectinib: Coadministration of itraconazole (a strong CYP3A inhibitor) with a single 100 mg dose of ROZLYTREK capsule increased entrectinib AUC0-INF by 6-fold and Cmax by 1.7-fold [see Drug Interactions (7.1)]. Coadministration of a moderate CYP3A inhibitor with ROZLYTREK capsule is predicted to increase entrectinib AUC0-Tau by 3-fold and Cmax by 2.9-fold. Based on physiologically based pharmacokinetic (PBPK) modelling, a similar magnitude of the effect is expected in children as young as 2 years old.

Effect of CYP3A Inducers on Entrectinib: Coadministration of rifampin (a strong CYP3A inducer) with a single 600 mg dose of ROZLYTREK capsule reduced entrectinib AUC0-INF by 77% and Cmax by 56% [see Drug Interactions (7.1)]. Coadministration of a moderate CYP3A inducer with ROZLYTREK capsule is predicted to reduce entrectinib AUC0-Tau by 56% and Cmax by 43%.

Effect of Gastric Acid Reducing Drugs on Entrectinib: Coadministration of a proton pump inhibitor (PPI), lansoprazole with a single 600 mg dose of ROZLYTREK capsule reduced entrectinib AUC by 25% and Cmax by 23%.

Coadministration of lansoprazole, with a single 600 mg dose of ROZLYTREK capsule as oral suspension in water increased entrectinib AUC by 25% and Cmax by 17%. These changes are not likely to be clinically significant.

Effect of Entrectinib on CYP Substrates: Coadministration of 600 mg dose of ROZLYTREK capsule once daily with oral midazolam (a sensitive CYP3A substrate) in patients increased the midazolam AUC by 50% but reduced midazolam Cmax by 21% [see Drug Interactions (7.1)].

Effect of Entrectinib on Transporters: Coadministration of a single 600 mg dose of ROZLYTREK capsule with digoxin [a sensitive P-glycoprotein (P-gp) substrate] increased digoxin Cmax by 28% and AUC by 18%.

In Vitro Studies

Entrectinib is not a substrate of P-gp or BCRP, but M5 is a substrate of P-gp and BCRP. Entrectinib and M5 are not substrates of OATP1B1 or OATP1B3.

13 NONCLINICAL TOXICOLOGY

13.1 Carcinogenesis, Mutagenesis, Impairment of Fertility

Carcinogenicity studies were not conducted with entrectinib. Entrectinib was not mutagenic in vitro in the bacterial reverse mutation (Ames) assay; however, an in vitro assay in cultured human peripheral blood lymphocytes did demonstrate a potential for abnormal chromosome segregation (aneugenicity). Entrectinib was not clastogenic or aneugenic in the in vivo micronucleus assay in rats and did not induce DNA damage in a comet assay in rats.

Dedicated fertility studies were not conducted with entrectinib. With the exception of dose-dependent decreases in prostate weight in male dogs, there were no effects on male and female reproductive organs observed in general toxicology studies conducted in rats and dogs at doses resulting in exposures of up to approximately 3.2-fold the human exposure (AUC) at the 600 mg dose.

14 CLINICAL STUDIES

14.1 ROS1-Positive Non-Small Cell Lung Cancer

The efficacy of ROZLYTREK was evaluated in a pooled subgroup of patients with ROS1-positive metastatic NSCLC who received ROZLYTREK at various doses and schedules (90% received ROZLYTREK 600 mg orally once daily) and were enrolled in one of three multicenter, single-arm, open-label clinical trials: ALKA, STARTRK-1 (NCT02097810) and STARTRK-2 (NCT02568267). To be included in this pooled subgroup, patients were required to have histologically confirmed, recurrent or metastatic, ROS1-positive NSCLC, ECOG performance status ≤ 2, measurable disease per RECIST v 1.1, ≥ 18 months of follow-up from first post-treatment tumor assessment, and no prior therapy with a ROS1 inhibitor. Identification of ROS1 gene fusion in tumor specimens was prospectively determined in local laboratories using either a fluorescence in situ hybridization (FISH), next-generation sequencing (NGS), or polymerase chain reaction (PCR) laboratory-developed tests. All patients were assessed for CNS lesions at baseline. The major efficacy outcome measures were overall response rate (ORR) and duration of response (DOR) according to RECIST v1.1 as assessed by Blinded Independent Central Review (BICR). Intracranial response according to Response Evaluation Criteria in Solid Tumors (RECIST v1.1) was assessed by BICR. Tumor assessments with imaging were performed every 8 weeks.

Efficacy was assessed in 92 patients with ROS1-positive NSCLC. The median age was 53 years (range: 27 to 86); female (65%); White (48%), Asian (45%), and Black (5%); and Hispanic or Latino (2.4%); never smoked (59%); and ECOG performance status 0 or 1 (88%). Ninety-nine percent of patients had metastatic disease, including 42% with CNS metastases; 96% had adenocarcinoma; 65% received prior platinum-based chemotherapy for metastatic or recurrent disease and no patient had progressed in less than 6 months following platinum-based adjuvant or neoadjuvant therapy. ROS1 positivity was determined by NGS in 79%, FISH in 16%, and PCR in 4%. Twenty-five percent had central laboratory confirmation of ROS1 positivity using an analytically validated NGS test.

Efficacy results are summarized in Table 12.

Table 12. Efficacy Results in ROS1-Positive NSCLC Patients per BICR Assessment
Efficacy Parameters | ROZLYTREK n = 92
Overall Response Rate (95% CI) | 74% (64, 83)
Complete Response | 15%
Partial Response | 59%
Duration of Response (DOR) [Observed DOR] | n = 68
Range (months) | 2.4, 55.2 [denotes ongoing response]
% DOR ≥ 9 months | 75%
% DOR ≥ 12 months | 57%
% DOR ≥ 18 months | 38%
Confidence Interval (CI) calculated using the Clopper-Pearson method.

Among the 92 patients, 10 had measurable CNS metastases at baseline as assessed by BICR and had not received radiation therapy to the brain within 2 months prior to study entry. Responses in intracranial lesions were observed in 7 of these 10 patients.

14.2 NTRK Gene Fusion-Positive Solid Tumors

Efficacy in Adult Patients

The efficacy of ROZLYTREK was evaluated in a pooled subgroup of adult patients with unresectable or metastatic solid tumors with a NTRK gene fusion enrolled in one of three multicenter, single-arm, open-label clinical trials: ALKA, STARTRK-1 (NCT02097810) and STARTRK-2 (NCT02568267). To be included in this pooled subgroup, patients were required to have progressed following systemic therapy for their disease, if available, or would have required surgery causing significant morbidity for locally advanced disease; measurable disease per RECIST v1.1; at least 2 years of follow-up from first post-treatment tumor assessment; and no prior therapy with a TRK inhibitor. Patients received ROZLYTREK at various doses and schedules (94% received ROZLYTREK 600 mg orally once daily) until unacceptable toxicity or disease progression. Identification of positive NTRK gene fusion status was prospectively determined in local laboratories or a central laboratory using various nucleic acid-based tests. The major efficacy outcome measures were ORR and DOR, as determined by a BICR according to RECIST v1.1. Intracranial response according to RECIST v1.1 as evaluated by BICR. Tumor assessments with imaging were performed every 8 weeks.

Efficacy was assessed in the first 54 adult patients with solid tumors with an NTRK gene fusion enrolled into these trials. The median age was 58 years (range: 21 to 83); female (59%); White (80%), Asian (13%) and Hispanic or Latino (7%); and ECOG performance status 0 (43%) or 1 (46%). Ninety-six percent of patients had metastatic disease, including 22% with CNS metastases, and 4% had locally advanced, unresectable disease. All patients had received prior treatment for their cancer including surgery (n = 43), radiotherapy (n = 36), or systemic therapy (n = 48). Forty patients (74%) received prior systemic therapy for metastatic disease with a median of 1 prior systemic regimen and 17% (n = 9) received 3 or more prior systemic regimens. The most common cancers were sarcoma (24%), lung cancer (19%), salivary gland tumors (13%), breast cancer (11%), thyroid cancer (9%), and colorectal cancer (7%). A total of 52 (96%) patients had an NTRK gene fusion detected by NGS and 2 (4%) had an NTRK gene fusion detected by other nucleic acid-based tests. Eighty-three percent of patients had central laboratory confirmation of NTRK gene fusion using an analytically validated NGS test.

Efficacy results are summarized in Tables 13, 14, and 15.

Table 13. Efficacy Results for Adult Patients with Solid Tumors Harboring NTRK Gene Fusions
Efficacy Parameter | ROZLYTREK n = 54
Overall Response Rate (95% CI) | 59% (45, 72)
Complete Response | 13%
Partial Response | 46%
Duration of Response [Observed DOR] | n = 32
Range (months) | 2.8, 47.8 [denotes ongoing response]
% with duration ≥ 6 months | 72%
% with duration ≥ 9 months | 66%
% with duration ≥ 12 months | 56%

Table 14. Efficacy by Tumor Type
Tumor Type | Patients n = 54 | ORR |  | DOR
Tumor Type | Patients n = 54 | % | 95% CI | Range (months)
Sarcoma | 13 | 46% | 19%, 75% | 2.8, 33.6 [denotes ongoing response]
Non-small cell lung cancer | 10 | 60% | 26%, 88% | 3.7, 47.8
Salivary (MASC) | 7 | 86% | 42%, 100% | 2.8, 38.5
Breast cancer | 6 | 83% | 36%, 100% | 4.2, 42.3
Thyroid cancer | 5 | 60% | NA | 7.9, 31.5
Colorectal cancer | 4 | 25% | NA | 15.1
Neuroendocrine cancers | 3 | CR | NA | 32.9
Pancreatic cancer | 3 | PR, PR | NA | 7.1, 12.9
Gynecological cancers | 2 | PR | NA | 38.2
Cholangiocarcinoma | 1 | PR | NA | 9.3
MASC: mammary analogue secretory carcinoma; NA = not applicable due to small numbers or lack of response; PR = partial response.

Table 15. Efficacy Results by NTRK Gene Fusion Partner
NTRK Partner | Patients n = 54 | ORR |  | DOR
NTRK Partner | Patients n = 54 | % | 95% CI | Range (months)
ETV6 – NTRK3 | 25 | 72% | 51%, 88% | 2.8, 47.8 [denotes ongoing response]
TPM3 – NTRK1 | 4 | 50% | 7%, 93% | 2.8, 15.1
TPR – NTRK1 | 4 | 100% | 40%, 100% | 5.6, 33.6
LMNA – NTRK1 | 2 | PR, PD | NA | 4.2
SQSTM1 – NTRK1 | 2 | PR, PD | NA | 18.8
PEAR1 – NTRK1 | 2 | SD, NE | NA | NA
EML4 – NTRK3 | 2 | PR, NE | NA | 13.2
CD74 – NTRK1 | 1 | PR | NA | 10.4
PLEKHA6 – NTRK1 | 1 | PR | NA | 9.3
CDC42BPA – NTRK1 | 1 | PR | NA | 29.4
EPS15L1 – NTRK1 | 1 | PR | NA | 3.7
RBPMS – NTRK3 | 1 | PR | NA | 4.6
ERC1 – NTRK1 | 1 | SD | NA | NA
PDIA3 – NTRK1 | 1 | SD | NA | NA
TRIM33 – NTRK1 | 1 | SD | NA | NA
AKAP13 – NTRK3 | 1 | SD | NA | NA
KIF7 – NTRK3 | 1 | SD | NA | NA
FAM19A2 – NTRK3 | 1 | PD | NA | NA
CGN – NTRK1 | 1 | NE | NA | NA
SQSTM1 – NTRK2 | 1 | NE | NA | NA
PR = partial response; PD = progressive disease; SD = stable disease; NA = not applicable due to small numbers or lack of response; NE = not evaluable.

Among the subset of patients who received prior systemic therapy for metastatic disease, the ORR was 53%, similar to that seen in the overall population. Among the 54 adult patients, 4 had measurable CNS metastases at baseline as assessed by BICR and had not received radiation therapy to the brain within 2 months of study entry. Responses in intracranial lesions were observed in 3 of these 4 patients.

Efficacy in Pediatric Patients

The efficacy of ROZLYTREK was evaluated in pediatric patients with unresectable or metastatic solid tumors with a NTRK gene fusion enrolled in one of two multicenter, open-label clinical trials: STARTRK-NG (NCT02650401) and TAPISTRY (NCT04589845). To be included in the analysis, patients were required to have received at least 1 dose of ROZLYTREK; measurable or evaluable disease at baseline; at least 6 months of follow-up; and no prior therapy with a TRK inhibitor. Patients received ROZLYTREK 20 mg to 600 mg based on body surface area (BSA) orally or via enteral feeding tube once daily in 4-week cycles until unacceptable toxicity or disease progression. The major efficacy outcome measure was overall response rate (ORR) as assessed by BICR according to RECIST v1.1 for extracranial tumors and according to Response Assessment in Neuro-Oncology (RANO) for primary central nervous system (CNS) tumors. An additional efficacy outcome measure was DOR as evaluated by BICR.

Efficacy was assessed in 33 pediatric patients with NTRK fusion-positive solid tumors treated with ROZLYTREK. The median age was 4 years (range: 2 months to 15 years); male (52%); White (58%), Asian (30%), other races (9%), Black or African American (3.0%), and Hispanic or Latino (9%). Seventy-one percent of patients had locally advanced disease and 29% had metastatic disease. Eighty-five percent of patients had received prior treatment for their cancer including surgery (n=20), radiotherapy (n=7) and/or systemic therapy (n=22). The sites for metastatic disease included other (4 patients), brain (3 patients) and lung (2 patients).

Efficacy results are summarized in Tables 16 and 17.

Table 16. Efficacy Results for Pediatric Patients with Solid Tumors Harboring NTRK Gene Fusions
Efficacy Parameter [Includes patients with measurable and evaluable disease. BICR analysis by RECIST v1.1 for solid tumors (16 patients) and by RANO criteria for primary CNS tumors (17 patients)] | ROZLYTREK n = 33
Overall Response Rate (95% CI) | 70% (51, 84)
Complete Response | 42%
Partial Response | 27%
Duration of Response [Observed DOR] | n = 23
Median in months (95% CI) | 25.4 (14.3, NE)
% with duration ≥ 12 months | 43%
NE = not estimable

Table 17. Efficacy Results for Pediatric Patients with Solid Tumors Harboring NTRK Gene Fusions by Tumor Type
Tumor Type | Patients n = 33 | ORR |  | DOR
Tumor Type | Patients n = 33 | % | 95% CI | Range (months)
Primary CNS [Median time to first objective response for patients with primary CNS tumors was 1.9 months] | 17 | 53% | 28%, 77% | 5.5, 30.4 [denotes ongoing response]
Infantile fibrosarcoma | 8 | 88% | 47%, 100% | 3.7, 24
Spindle Cell | 6 | 100% | 54%, 100% | 3.7, 12.9
Sarcoma (other) | 1 | 0% [Patient with evaluable but non-measurable disease at baseline] | NA | NA
Melanoma | 1 | 100% | NA | 42.4
NA = not applicable due to small numbers or lack of response

Table 18. Efficacy Results for Pediatric Patients with Solid Tumors Harboring NTRK by Gene Fusion Partner
NTRK Partner | Patients n = 33 | ORR |  | DOR
NTRK Partner | Patients n = 33 | % | 95% CI | Range (months)
ETV6 – NTRK3 | 7 | 86% | 42%, 100% | 11.9 - 42.4 [denotes ongoing response]
LMNA – NTRK1 | 5 | 80% | 28%, 99% | 7.4 - 12.9
TPM3 – NTRK1 | 3 | 100% | 29%, 100% | 3.7 - 24.0
TPR – NTRK1 | 3 | 67% | 9%, 99% | 8.1 - 14.3
EML4-NTRK3 | 2 | 50% | 1.3%, 99% | 13.8
BCAN-NTRK1 | 1 | CR | NA | 11.8
EML1-NTRK2 | 1 | CR | NA | 11.8
QKI-NTRK2 | 1 | CR | NA | 11.1
TFG-NTRK3 | 1 | CR | NA | 3.7
KANK1-NTRK2 | 1 | PR | NA | 5.5
KIF5B-NTRK2 | 1 | PR | NA | 12.9
TNS3-NRTK2 | 1 | PR | NA | 9.5
ARHGEF2-NTRK1 | 1 | SD | NA | NA
KIF21B-NTRK1 | 1 | SD | NA | NA
BCR-NTRK2 | 1 | SD | NA | NA
GKAP1-NTRK2 | 1 | SD | NA | NA
DNM3-NTRK2 | 1 | PD | NA | NA
PARP6-NTRK3 | 1 | PD | NA | NA
PR = partial response; PD = progressive disease; SD = stable disease; NA = not applicable due to small numbers or lack of response

16 HOW SUPPLIED/STORAGE AND HANDLING

Capsules

How Supplied

- 100 mg hard capsules: Size 2 yellow opaque, with "ENT 100" printed in blue ink; available in HDPE bottles of 30 capsules: NDC 50242-091-30
- 200 mg hard capsules: Size 0 orange opaque, with "ENT 200" printed in blue ink; available in HDPE bottles of 90 capsules: NDC 50242-094-90

Storage:

Store at 20°C to 25°C (68°F to 77°F); excursions permitted between 15°C to 30°C (59°F to 86°F) [See USP Controlled Room Temperature].

Store ROZLYTREK capsules in the original container and keep the bottle tightly closed in order to protect from moisture.

Storage time should not exceed 2 hours (below 30°C (86°F)) if capsules are prepared as an oral suspension using drinking water or milk. Discard any unused suspension if not used within 2 hours of preparation.

Pellets

How Supplied

- ROZLYTREK oral pellets are supplied as brownish orange to grayish orange, round pellets, available in: 42-count carton (each packet contains 50 mg entrectinib): NDC 50242-623-42

Storage:

Store at 20°C to 25°C (68°F to 77°F); excursions permitted between 15°C to 30°C (59°F to 86°F) [See USP Controlled Room Temperature].

Store ROZLYTREK oral pellets in the original container in order to protect from moisture.

17 PATIENT COUNSELING INFORMATION

Advise the patient to read the FDA-approved patient labeling (Patient Information and Instructions for Use).

Congestive Heart Failure

- Inform patients of the risks of CHF and advise patients to contact their healthcare provider immediately for any new or worsening signs or symptoms of CHF [see Warnings and Precautions (5.1)].

Central Nervous System Effects

- Advise patients to inform their healthcare provider if they experience new or worsening central nervous system symptoms. Instruct patients not to drive or operate hazardous machinery if they are experiencing CNS adverse reactions [see Warnings and Precautions (5.2)].

Skeletal Fractures

- Inform patients that bone fractures have been reported in patients taking ROZLYTREK. Advise patients to report symptoms such as pain, changes in mobility, or deformity to their healthcare provider [see Warnings and Precautions (5.3)].

Hepatotoxicity

- Advise patients that they will need to undergo laboratory tests to monitor liver function and to immediately report symptoms of hepatotoxicity [see Warnings and Precautions (5.4)].

Hyperuricemia

- Advise patients to inform their healthcare provider if they experience signs or symptoms associated with hyperuricemia [see Warnings and Precautions (5.5)].

QT Interval Prolongation

- Inform patients of the risks of QT interval prolongation and to advise patients to contact their healthcare provider immediately for any symptoms of QT interval prolongation [see Warnings and Precautions (5.6)].

Vision Disorders

- Advise patients to inform their healthcare provider if they experience visual changes [see Warnings and Precautions (5.7)].

Embryo-Fetal Toxicity

- Advise pregnant women and females of reproductive potential of the potential risk to a fetus. Advise females to inform their healthcare provider of a known or suspected pregnancy [see Warnings and Precautions (5.8), Use in Specific Populations (8.1, 8.3)].
- Advise females of reproductive potential to use effective contraception during treatment with ROZLYTREK and for 5 weeks after the last dose.
- Advise male patients with female partners of reproductive potential to use effective contraception during treatment and for 3 months after the last dose.

Lactation

- Advise females not to breastfeed during treatment with ROZLYTREK and for 1 week after the last dose [see Use in Specific Populations (8.2)].

Drug Interactions

- Advise patients to inform their healthcare providers of all concomitant medications, including prescription medicines, over-the-counter drugs, vitamins, and herbal products. Advise patients to avoid grapefruit juice while taking ROZLYTREK [see Drug Interactions (7)].

Administration

- Instruct patients and caregivers to read the Instructions for Use before the patient starts using ROZLYTREK, and each time the patient gets a refill as there may be new information they need to know.
- For capsules taken as an oral suspension or for administration by enteral tube: Provide patients and caregivers with a measuring device (e.g., oral syringe, measuring cup) to prepare and measure their prescribed dose if taking ROZLYTREK capsules as an oral suspension. Instruct patients and/or caregivers how to use the measuring device provided and inform patients they may need to measure out a portion of oral suspension prepared to receive the prescribed dosage. If not taken immediately after preparation, store no longer than 2 hours at room temperature below 30°C (86°F) [see Dosage and Administration (2.9)].
- For pellets: Instruct patients and caregivers that ROZLYTREK oral pellets should be sprinkled on one or more spoonfuls of a soft food (e.g., applesauce, yogurt, or pudding) and must be taken within 20 minutes of preparation. Oral pellets are not suitable for enteral administration due to potential for clogging in tubing [see Dosage and Administration (2.9)].
- Instruct patients if they miss a dose to make up that dose unless the next dose is due within 12 hours.
- Instruct patients if they vomit immediately after taking a dose of ROZLYTREK to take a dose as soon as possible [Dosage and Administration (2.4)].

ROZLYTREK (entrectinib)

Distributed by:
Genentech USA, Inc.
A Member of the Roche Group
1 DNA Way
South San Francisco, CA 94080-4990

ROZLYTREK® is a registered trademark of Genentech, Inc.

©2024 Genentech, Inc. All rights reserved.

PATIENT INFORMATION

ROZLYTREK® (roz lye' trek)
(entrectinib)
capsules

ROZLYTREK® (roz lye' trek)
(entrectinib)
oral pellets

What is the most important information I should know about ROZLYTREK?

ROZLYTREK may cause serious side effects, including:

- Congestive heart failure. ROZLYTREK may cause congestive heart failure or make the congestive heart failure that you already have worse. Your healthcare provider will do tests before your treatment and may do tests during your treatment with ROZLYTREK to check your heart function. Tell your healthcare provider right away if you have any of the following signs and symptoms of congestive heart failure:

- persistent coughing or wheezing
- trouble breathing when lying down
- sudden weight gain

- increasing shortness of breath
- tiredness, weakness, or fatigue
- swelling in ankles, feet, or legs

- Central nervous system (CNS) effects. ROZLYTREK may cause dizziness, changes in your mood, or may affect how you think and cause confusion, hallucinations, and problems with concentration, attention, memory, speaking, understanding what your hear or read, and sleep. Tell your healthcare provider right away if you have any of these symptoms.
- Bone fractures. ROZLYTREK may increase your risk for bone fractures. Bone fractures may happen with or without a fall or other injury. Tell your healthcare provider if you develop pain, changes in movement, or bone abnormalities.
- Liver problems (hepatotoxicity). Your healthcare provider will do blood tests to check your liver function during treatment with ROZLYTREK. Tell your healthcare provider right away if you develop any of the following symptoms of liver problems:

- loss of appetite
- nausea or vomiting
- pain in your upper right stomach area

- yellowing of your skin or the white part of your eyes
- dark urine

- Increased uric acid level in your blood (hyperuricemia). ROZLYTREK may cause too much uric acid in your blood. Your healthcare provider will do tests before and during your treatment with ROZLYTREK to check the uric acid level in your blood. Your healthcare provider may prescribe medications if you have high blood uric acid levels. Tell your healthcare provider if you develop any of the following symptoms of hyperuricemia:

- red, hot, tender, or swollen joints, especially in your big toe
- pain in your stomach-area or sides

- nausea or vomiting
- pink or brown urine

- Changes in the electrical activity of your heart called QT prolongation. QT prolongation can cause irregular heartbeats that can be life-threatening. Your healthcare provider will do tests before and during your treatment with ROZLYTREK to check the electrical activity of your heart and your body salts (electrolytes). Tell your healthcare provider right away if you feel faint, lightheaded, dizzy, or feel your heart beating irregularly or fast during your treatment with ROZLYTREK. These may be symptoms related to QT prolongation.
- Vision problems. ROZLYTREK may cause vision problems. Your healthcare provider may stop ROZLYTREK and refer you to an eye specialist if you develop severe vision problems during treatment with ROZLYTREK. Tell your healthcare provider right away if you have any loss of vision or any change in vision, including:

- double vision
- blurry vision
- new or increased floaters

- seeing flashes of light
- light hurting your eyes

Your healthcare provider may temporarily stop treatment, decrease your dose, or permanently stop ROZLYTREK if you develop certain side effects during treatment with ROZLYTREK.

What is ROZLYTREK?
ROZLYTREK is a prescription medicine used to treat:

- Adults with non-small cell lung cancer (NSCLC) that has spread to other parts of the body and is caused by an abnormal ROS1 gene.
- Adults and children 1 month of age and older with solid tumors (cancer) that:
  - are caused by certain abnormal NTRK genes, and
  - have spread or if surgery to remove their cancer is likely to cause severe complications, and
  - there is no satisfactory alternative treatment option or the cancer grew or spread on other treatment.

It is not known if ROZLYTREK is safe and effective in children with ROS1 NSCLC or in children under 1 month of age with NTRK solid tumors.

Before taking ROZLYTREK, tell your healthcare provider about all your medical conditions, including if you:

- have liver or kidney problems
- have any heart problems, including a condition called long QT syndrome
- have nervous system (neurological) problems
- have or have had eye or vision problems
- are pregnant or plan to become pregnant. ROZLYTREK can cause harm to your unborn baby. Tell your healthcare provider right away if you become pregnant or think you may be pregnant during treatment with ROZLYTREK.
  Females who can become pregnant:
  - Your healthcare provider will do a pregnancy test before you start treatment with ROZLYTREK.
  - Use effective birth control (contraception) during treatment with ROZLYTREK and for at least 5 weeks after the last dose.
  Males with female partners that can become pregnant:
  - Use effective birth control (contraception) during treatment with ROZLYTREK and for 3 months after the last dose.
- are breastfeeding or plan to breastfeed. It is not known if ROZLYTREK passes into your breast milk. Do not breastfeed during treatment with ROZLYTREK and for 7 days (1 week) after the last dose of ROZLYTREK. Talk to your healthcare provider about the best way to feed your baby during this time.

Tell your healthcare provider about all the medicines you take, including prescription and over-the-counter medicines, vitamins, or herbal supplements.
Taking ROZLYTREK with certain other medicines may affect the amount of ROZLYTREK or other medicine in your blood and may cause side effects or affect the way that ROZLYTREK or the other medicine work. Know the medicines you take. Keep a list of them to show to your healthcare provider and pharmacist when you get a new medicine.

How should I take ROZLYTREK?

- Take ROZLYTREK exactly as your healthcare provider tells you. Do not change your dose or stop taking ROZLYTREK unless your healthcare provider tells you to.
- Your healthcare provider may change your dose, temporarily stop, or permanently stop treatment with ROZLYTREK if you develop certain side effects.
- Take ROZLYTREK 1 time each day with or without food.
- Your healthcare provider will either prescribe:
  - ROZLYTREK capsules to be swallowed whole or prepared and taken or given as a suspension or
  - ROZLYTREK oral pellets to be sprinkled on 1 or more spoonfuls of soft food before taking.
- If you miss a dose of ROZLYTREK, take it as soon as you remember. If your next dose is due within 12 hours, skip the missed dose and take your next dose at your regular time.
- If you vomit right after taking a dose of ROZLYTREK, you may take the dose again.

See the detailed Instructions for Use for information on how to give or take a dose of ROZLYTREK capsules or oral pellets.
If you are taking whole ROZLYTREK capsules:

- Swallow whole capsules with drinking water, as directed by your healthcare provider.
- Do not crush or chew the capsule.

If you are taking ROZLYTREK capsules prepared as a suspension:

- Carefully open the prescribed number of capsules and pour the contents into room temperature drinking water or milk. Your healthcare provider will tell you how much water or milk to use, how much suspension to take or give, and provide you with a measuring device like an oral syringe or measuring cup.
- Let the suspension sit for 15 minutes before taking.
- You may need to take less suspension than you prepared depending on your prescribed dose.
- Drink water after taking the suspension to make sure you have swallowed all the medicine.
- If you do not take the suspension right away, you can store it for up to 2 hours at room temperature below 86°F (30°C). Throw away (discard) the unused suspension if it is not used within 2 hours of preparation.
- If you cannot swallow and have a gastric or nasogastric tube, the suspension can be given through the feeding tube.

If you are taking ROZLYTREK oral pellets:

- Sprinkle the prescribed number of packets of pellets on 1 or more spoonfuls of a soft food like applesauce, yogurt, or pudding, and take within 20 minutes of sprinkling the pellets on the soft food.
- Do not crush or chew the pellets to avoid a bitter taste.
- Drink water after taking the prescribed dose to make sure you have swallowed all the medicine.
- Use the whole packet of pellets. Do not use part of the packet to try to prepare a dose.
- Do not use the pellets to make a suspension.
- Do not give the pellets through a gastric or nasogastric tube because the pellets may clog the feeding tube.

What should I avoid while taking ROZLYTREK?

- You should not drink grapefruit juice or eat grapefruit during your treatment with ROZLYTREK. It may increase the amount of entrectinib in your blood to a harmful level and increase your chance of getting side effects.
- Do not drive or operate heavy machinery until you know how ROZLYTREK affects you. If you experience dizziness, fainting, tiredness, blurred vision, memory loss, changes in mental status, confusion, or hallucinations, do not drive or operate heavy machines until your symptoms resolve.

What are the possible side effects of ROZLYTREK?
ROZLYTREK may cause serious side effects, including:

- See "What is the most important information I should know about ROZLYTREK?"

The most common side effects of ROZLYTREK include:

- tiredness
- constipation
- change in taste
- swelling
- dizziness
- diarrhea

- nausea
- abnormal touch sensation
- shortness of breath
- muscle pain
- confusion, mental status changes, memory problems, and hallucinations

- weight gain
- cough
- vomiting
- fever
- joint pain
- vision changes

These are not all the possible side effects of ROZLYTREK.
Call your doctor for medical advice about side effects. You may report side effects to FDA at 1-800-FDA-1088.

How should I store ROZLYTREK?
ROZLYTREK capsules

- Store ROZLYTREK at room temperature between 68°F to 77°F (20°C to 25°C).
- Store ROZLYTREK capsules in the original container and keep the bottle tightly closed to protect from moisture.

ROZLYTREK oral pellets

- Store ROZLYTREK oral pellets at room temperature between 68°F to 77°F (20°C to 25°C).
- Store ROZLYTREK oral pellets in the original container to protect from moisture.

Keep ROZLYTREK and all medicines out of the reach of children.

General information about the safe and effective use of ROZLYTREK.
Medicines are sometimes prescribed for purposes other than those listed in a Patient Information leaflet. Do not use ROZLYTREK for a condition for which it was not prescribed. Do not give ROZLYTREK to other people, even if they have the same symptoms that you have. It may harm them. You can ask your pharmacist or healthcare provider for information about ROZLYTREK that is written for health professionals.

What are the ingredients in ROZLYTREK?
Active ingredient: entrectinib
Inactive ingredients:
Capsules: tartaric acid, lactose anhydrous, hypromellose, crospovidone, microcrystalline cellulose, colloidal silicon dioxide, and magnesium stearate.

- Yellow opaque capsule shell: hypromellose, titanium dioxide, and yellow iron oxide
- Orange opaque capsule shell: hypromellose, titanium dioxide, and FD&C Yellow No. 6
- Printing ink: shellac, propylene glycol, strong ammonia solution, and FD&C Blue No. 2 aluminum lake

Pellets: tartaric acid, microcrystalline cellulose, colloidal silicon dioxide, croscarmellose sodium, sodium stearyl fumarate, mannitol, and magnesium stearate

- Film-coating: polyvinyl alcohol (partially hydrolyzed), titanium dioxide, polyethylene glycol 3350, talc, yellow iron oxide, red iron oxide, and ferrosoferric oxide

Distributed by: Genentech, Inc., A Member of the Roche Group, 1 DNA Way, South San Francisco, CA 94080-4990
ROZLYTREK® is a registered trademark of Genentech, Inc. ©2024 Genentech, Inc.
For more information, go to www.ROZLYTREK.com or call 1-877-436-3683.

This Patient Information has been approved by the U.S. Food and Drug Administration.

Revised 1/2024

INSTRUCTIONS FOR USE
ROZLYTREK® [roz lye trek]
(entrectinib)
capsules, for oral use

This Instructions for Use contains information on how to prepare and take or give ROZLYTREK capsules.

Before Starting

Read this Instructions for Use before giving ROZLYTREK capsules for the first time and each time you get a refill. There may be new information.

ROZLYTREK capsules can be swallowed whole or prepared as a suspension and taken or given by mouth or through a nasogastric tube (NG tube) or gastrostomy tube (G tube) feeding tube.

Important Information You Need to Know Before Taking or Giving ROZLYTREK Capsules

- Your healthcare provider or pharmacist should show you how to correctly prepare and take or give a dose of ROZLYTREK capsules. Always take or give ROZLYTREK capsules exactly as your healthcare provider tells you.
- Do not take or give ROZLYTREK to someone else until you have been shown how to properly prepare and take or give ROZLYTREK.
- Wash your hands before and after preparing, taking, or giving ROZLYTREK.
- Check the expiration date and check the product for damage before use. Do not use if expired or damaged.

Dosing of ROZLYTREK capsules to be swallowed whole

- Your healthcare provider will decide the right dose of ROZLYTREK for you or your child.
- Your healthcare provider will tell you what your daily dose of ROZLYTREK is.
- Swallow ROZLYTREK capsules whole, with or without food.
- Swallow whole capsules with drinking water, as directed by your healthcare provider.
- Do not crush or chew the capsules.

Dosing of ROZLYTREK capsules prepared as a suspension to be taken by mouth or through a feeding tube

If you or your child cannot swallow capsules whole, ROZLYTREK capsules can be prepared as a suspension and taken or given by mouth or through a feeding tube. For doses of 3 mL or higher, a NG or G feeding tube size 8 French or larger should be used.

Your healthcare provider or pharmacist will show you how to prepare and take or give a dose of ROZLYTREK capsules prepared as a suspension.

Table 1 shows the prescribed dose, the number and strength of capsules needed, the amount of water or milk needed to mix the capsules, and the amount of suspension needed to give for the prescribed dose.

Your healthcare provider will tell you the number of capsules to use, the amount of liquid needed to mix the capsules, and the amount of suspension (mL) to take or give to get the correct dose of ROZLYTREK.

You may need to measure a smaller amount of suspension than you prepared to take or give the correct prescribed dose of ROZLYTREK.

Table 1. Preparation of ROZLYTREK capsules as a suspension
Prescribed dose of ROZLYTREK to be given | Number of 100 mg or 200 mg capsules needed | Amount of water or milk needed to mix the capsules | Amount of suspension to take or give
20 mg | One 100 mg | 5 mL | 1 mL
30 mg | One 100 mg | 5 mL | 1.5 mL
40 mg | One 100 mg | 5 mL | 2 mL
50 mg | One 100 mg | 5 mL | 2.5 mL
60 mg | One 100 mg | 5 mL | 3 mL
70 mg | One 100 mg | 5 mL | 3.5 mL
80 mg | One 100 mg | 5 mL | 4 mL
90 mg | One 100 mg | 5 mL | 4.5 mL
100 mg | One 100 mg | 5 mL | 5 mL
110 mg | One 200 mg | 10 mL | 5.5 mL
120 mg | One 200 mg | 10 mL | 6 mL
130 mg | One 200 mg | 10 mL | 6.5 mL
140 mg | One 200 mg | 10 mL | 7 mL
150 mg | One 200 mg | 10 mL | 7.5 mL
200 mg | One 200 mg | 10 mL | 10 mL
300 mg | Three 100 mg | 15 mL | 15 mL
400 mg | Two 200 mg | 20 mL | 20 mL
600 mg | Three 200 mg | 30 mL | 30 mL

Supplies needed to prepare and take or give ROZLYTREK as a suspension:

- the number of capsules needed for your prescribed dose
- a clean empty cup
- a paper towel
- a cup of room temperature drinking water or milk
- an oral syringe (provided by your healthcare provider or pharmacist)

Preparing ROZLYTREK capsules as a suspension

Step 1. Wash your hands.

Step 2. Count the number of capsules you will need to give the prescribed dose.

Step 3. Place a clean empty cup on a paper towel.

Figure A

Step 4. Tap the capsules to loosen the contents inside (medicine).

Step 5. While holding each capsule above the clean cup, open the capsule by gently pressing in on the capsule and twisting both sides apart.
Pour the medicine into the clean cup (Figure A).

Step 6. Tap both sides of the capsule shell and check to make sure all the medicine has gone into the cup.

- If the medicine is spilled outside of the cup, go to Step D1 for clean-up instructions, then start over at Step 1.

Step 7. Push the syringe plunger all the way down to remove any air in the oral syringe (Figure B).

Figure B

Step 8. Place the syringe tip into the room temperature cup of drinking water or milk.
Measure the proper amount of liquid (mL) by pulling up on the syringe plunger to draw the liquid into the syringe (Figure C).
Your healthcare provider will tell you how much liquid to use.
Do not use any other type of liquid.

Figure C

Step 9. Check that the correct amount of liquid (mL) is in the syringe (Figure D).

Figure D

Step 10. Add the liquid to the cup that contains the medicine by holding the barrel of the syringe and pushing the syringe plunger all the way down (Figure E).

Figure E

Step 11. Let the mixture sit for 15 minutes (Figure F).
Note: It is important to do this to get an even mixture, otherwise you may not get the correct dose.

Figure F

Step 12. Swirl the cup several times to evenly mix the medicine in the liquid (Figure G).
Note: The medicine does not dissolve in the liquid and the suspension will be cloudy if you have used water.

Figure G

Step 13. Push the syringe plunger all the way down to remove any air in the syringe (Figure H).

Figure H

Step 14. Swirl the cup of medicine again before placing the syringe in the cup (Figure I).

Figure I

Step 15. Place the syringe tip right away into the cup and slowly pull up the plunger to draw up the correct amount (mL) of suspension (Figure J).
Do not wait to draw up the suspension. If it sits for too long, the medicine may settle to the bottom, and you may not get the correct dose.

Figure J

Step 16. Check that the correct amount of suspension (mL) is in the syringe (Figure K).

Figure K

Step 17. With the tip of the syringe pointing up, check that:

- you have withdrawn the correct amount (mL)
- there are no large bubbles (Figure L)

Note: If you have not withdrawn the correct amount (mL), or if there are large bubbles inside:

- put the syringe into the cup again
- push the suspension back into the cup
- then draw up the suspension again (start at Step 12).

Give ROZLYTREK right away after it is drawn up into the syringe.
NOTE: Throw away the suspension if you do not take or give it within 2 hours of preparing the suspension and start over at step 1.

Figure L

Giving ROZLYTREK capsules prepared as a suspension by mouth

Step A1. Sit your child upright when you give a dose of ROZLYTREK by mouth (Figure M).
Place the oral syringe into the mouth with the tip along either cheek.
Slowly push the plunger all the way down.
Giving ROZLYTREK too fast may cause choking.

Figure M

Step A2. Check that there is no suspension left in the oral syringe (Figure N).
If suspension remains in the oral syringe, repeat step A1.

Figure N

Step A3. Give sips of water right after taking or giving the prescribed dose of ROZLYTREK (Figure O).
You can breastfeed or give your child milk if they still taste the medicine after you give the dose.
Go to Step D1 for clean-up instructions.

Figure O

Giving ROZLYTREK capsules prepared as a suspension through a gastrostomy tube (G tube)

To take or give ROZLYTREK through a G tube review the manufacturer's instructions and consult your healthcare provider. Make sure that the tube is at least 8 French or larger to prevent clogging of the tube if your dose (amount of suspension) is 3 mL or higher.
To take or give ROZLYTREK doses of 3 mL or higher, split the dose in half and give it in 2 parts. Flush the tube with the same amount of water or milk after giving each part.
To take or give ROZLYTREK doses of 30 mL, split the dose into at least three 10 mL parts. Flush the tube with the same amount of water or milk after giving each part.

Step B1
Place the oral syringe tip into the G tube. Slowly push the plunger all the way down to give ROZLYTREK (Figure P).

Figure P

Step B2
Check that there is no suspension left in the oral syringe (Figure Q).
If suspension remains in the oral syringe, repeat step B1.

Figure Q

Step B3
Flush the G tube with water or milk right after giving ROZLYTREK (Figure R).
If you need to split the amount of suspension to give it through the G tube, also split the amount of water or milk you use to flush the tube in the same way.
Ask your healthcare provider if you are not sure how much water or milk to use to flush the G tube.
Go to Step D1 for clean up instructions.

Figure R

Giving ROZLYTREK capsules prepared as a suspension through a nasogastric tube (NG tube)

If you are giving ROZLYTREK through an NG tube, review the manufacturer instructions and consult your healthcare provider. Make sure that the tube is at least 8 French or larger to prevent clogging of the tube if your dose (amount of suspension) is 3 mL or higher.
To take or give ROZLYTREK doses of 3 mL or higher, split the dose in half and give it in 2 parts. Flush the tube with the same amount of water or milk after giving each part.
To take or give ROZLYTREK doses of 30 mL, split the dose into at least three 10 mL parts. Flush the tube with the same amount of water or milk after giving each part.

Step C1
Place the syringe tip into the NG tube. Slowly press the plunger all the way down to give ROZLYTREK (Figure S).

Figure S

Step C2
Check that there is no suspension left in the syringe (Figure T).
If suspension remains in the syringe, repeat step C1.

Figure T

Step C3
Flush the NG tube with water or milk right after giving ROZLYTREK (Figure U).
If you need to split the amount of suspension to give it through the NG tube, also split the amount of water or milk you use to flush the tube in the same way.
Ask your healthcare provider if you are not sure how much water or milk to use to flush the NG tube.
Go to Step D1 for clean up instructions.

Figure U

Cleaning up and disposing of ROZLYTREK

Step D1

- Wash your hands and all the items used to give ROZLYTREK.
- Remove the syringe plunger from the syringe barrel.
- Use only clean water to rinse the syringe parts and the cup used to prepare the suspension. Let all items dry before the next use.
- Put the syringe plunger back into the syringe barrel when dry.
- Throw away (discard of) the disposable items in your household trash.

Storing ROZLYTREK

- Store ROZLYTREK capsules at room temperature between 68°F to 77°F (20°C to 25°C).
- Do not store ROZLYTREK prepared as a suspension for more than 2 hours at room temperature below 86°F (30°C). Throw away any unused suspension if it is not used within 2 hours of preparation.
- Store ROZLYTREK capsules in the original container and keep the bottle tightly closed to protect from moisture.

Keep ROZLYTREK and all medicines out of the reach of children.

Distributed by:
Genentech USA, Inc.
A Member of the Roche Group
1 DNA Way
South San Francisco, CA 94080-4990

ROZLYTREK® is a registered trademark of Genentech, Inc.

©2023 Genentech, Inc.

For more information, go to www.ROZLYTREK.com or call 1-877-436-3683.

This Instructions for Use has been approved by the U.S. Food and Drug Administration.

Issued: 10/2023

INSTRUCTIONS FOR USE
ROZLYTREK® [roz lye trek]
(entrectinib)
oral pellets

This Instructions for Use contains information on how to prepare and take or give ROZLYTREK oral pellets.

Before Starting

Read this Instructions for Use before giving ROZLYTREK oral pellets for the first time and each time you get a refill. There may be new information.

Sprinkle ROZLYTREK oral pellets on 1 or more spoonfuls of a soft food before taking or giving.

Do not use ROZLYTREK oral pellets to prepare a suspension.

Do not give or take ROZYLTREK oral pellets through a gastrostomy tube (G Tube) or nasogastric tube (NG Tube) because the pellets may clog the feeding tube.

Important Information You Need to Know Before Preparing and Taking or Giving ROZLYTREK Oral Pellets

- Your healthcare provider should show you how to properly prepare and take or give a daily dose of ROZLYTREK oral pellets. Always take or give ROZLYTREK oral pellets exactly as your healthcare provider tells you.
- Do not take ROZLYTREK oral pellets or give it to someone else until you have been shown how to properly prepare and take or give ROZLYTREK.
- Wash your hands before and after preparing, taking, or giving ROZLYTREK.
- Check the expiration date and check the product for damage before use. Do not use if expired or damaged.

Dosing ROZLYTREK oral pellets

- Your healthcare provider will decide the right dose of ROZLYTREK for you or your child.
- ROZLYTREK oral pellets come in a carton with 42 packets. Each packet contains 50 mg of ROZLYTREK.
- Use the whole packet of pellets. Do not use part of the packet to try to prepare a dose.
- Sprinkle the prescribed number of packets on 1 or more spoonfuls of soft food and take or give within 20 minutes of sprinkling the pellets on the soft food.
- Do not crush or chew the pellets to avoid a bitter taste.

Supplies needed to prepare and take or give ROZLYTREK oral pellets:

- the number of packets needed for your prescribed dose
- a clean spoon
- a paper towel or clean plate
- soft food like applesauce, yogurt, or pudding

Preparing to take or give ROZLYTREK oral pellets

Step 1. Wash your hands.

Step 2. Get a soft food like applesauce, yogurt, or pudding to use to take or give ROZLYTREK oral pellets.

Step 3. Count the number of packets you will need to give the prescribed dose.

- Tap the packets to make sure that the pellets are on one side of the packet.
- Hold the side of the packet where the pellets are tapped and open the other side of the packet with your other hand or with scissors (Figure A).

Note: Make sure that you do not cut the pellets with scissors.

Figure A

Step 4. Get a spoonful of the soft food and hold the spoonful above a paper towel or clean plate.

- Sprinkle the prescribed number of packets on the spoonful of soft food (Figure B).
- Tap the packets to make sure all pellets are sprinkled on the food.

Note: You may need to use more than 1 spoonful of soft food to give the prescribed dose. If you need to use another spoonful, finish step 5 and then repeat steps 4 and 5.

Figure B

Giving ROZLYTREK oral pellets

Step 5. Take or give the spoonful of food with the pellets sprinkled on it right away (Figure C).
Take or give the spoonful of soft food within 20 minutes after sprinkling the pellets on it if you cannot take or give it right way.
Note: If you leave the pellets in the soft food for too long it may dissolve the coating and cause a bitter taste. Do not crush or chew the pellets because this may also cause a bitter taste.
Throw away the soft food with the pellets sprinkled on it if you do no not take it within 20 minutes and prepare a new dose (start at Step 1).
If you need more than 1 spoonful of soft food to take or give the prescribed dose, repeat steps 4 and 5.

Figure C

Step 6. Give sips of water after taking or giving the prescribed dose to make sure all the pellets are swallowed. (Figure D).
A meal or drink can be given after taking the ROZLYTREK dose to help with the taste.

Figure D

Step 7. Check the mouth to make sure that all of the pellets were swallowed (Figure E). If not all pellets are swallowed, give more sips of water.

Figure E

Cleaning up and disposing of ROZLYTREK oral pellets

- Wash your hands and all the items used to give ROZLYTREK.
- Throw away (discard of) the disposable items in your household trash.

Storing ROZLYTREK oral pellets

- Store ROZLYTREK oral pellets at room temperature between 68°F to 77°F (20°C to 25°C)
- Store ROZLYTREK oral pellets in the original container to protect from moisture.

Keep ROZLYTREK and all medicines out of the reach of children.

Distributed by:
Genentech USA, Inc.
A Member of the Roche Group
1 DNA Way
South San Francisco, CA 94080-4990

ROZLYTREK® is a registered trademark of Genentech, Inc.

©2023 Genentech, Inc.

For more information, go to www.ROZLYTREK.com or call 1-877-436-3683.

This Instructions for Use has been approved by the U.S. Food and Drug Administration.

Issued: 10/2023

PRINCIPAL DISPLAY PANEL - 100 mg Capsules Bottle Carton

NDC 50242-091-30

Rozlytrek®
(entrectinib)
capsules

100 mg

PHARMACIST: Dispense with
the included Instructions for Use

30 capsules

Rx only

Genentech

11013439

PRINCIPAL DISPLAY PANEL - 200 mg Capsules Bottle Carton

NDC 50242-094-90

Rozlytrek®
(entrectinib)
capsules

200 mg

PHARMACIST: Dispense with
the included Instructions for Use

90 capsules

Rx only

Genentech

11013451

PRINCIPAL DISPLAY PANEL - 50 mg Pellets Packet Carton

NDC 50242-623-42

Rozlytrek®
(entrectinib)
oral pellets

50 mg

42 packets

Rx only

Genentech

11006603